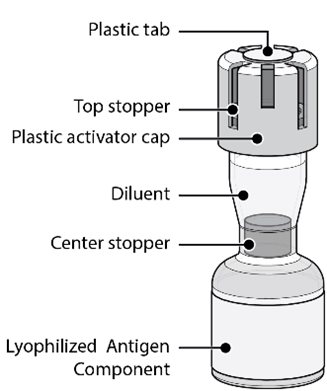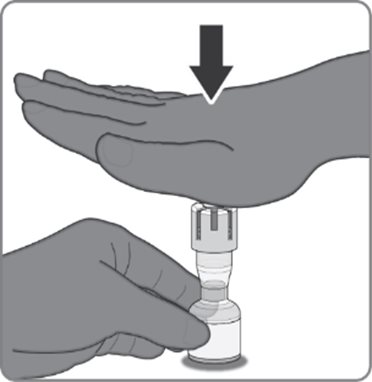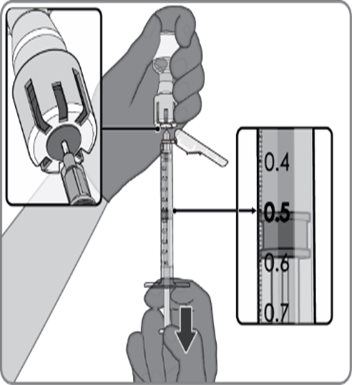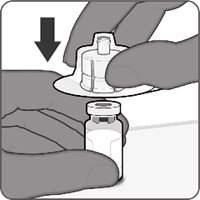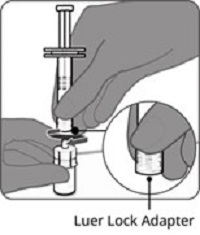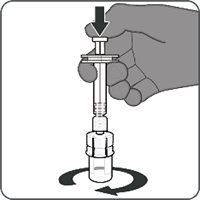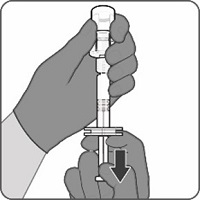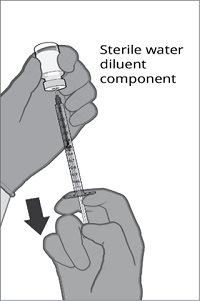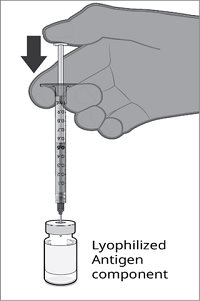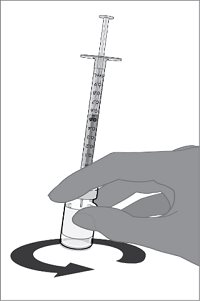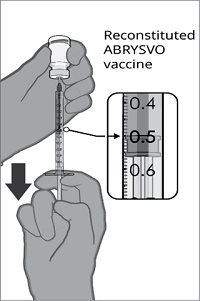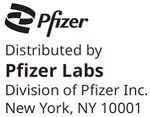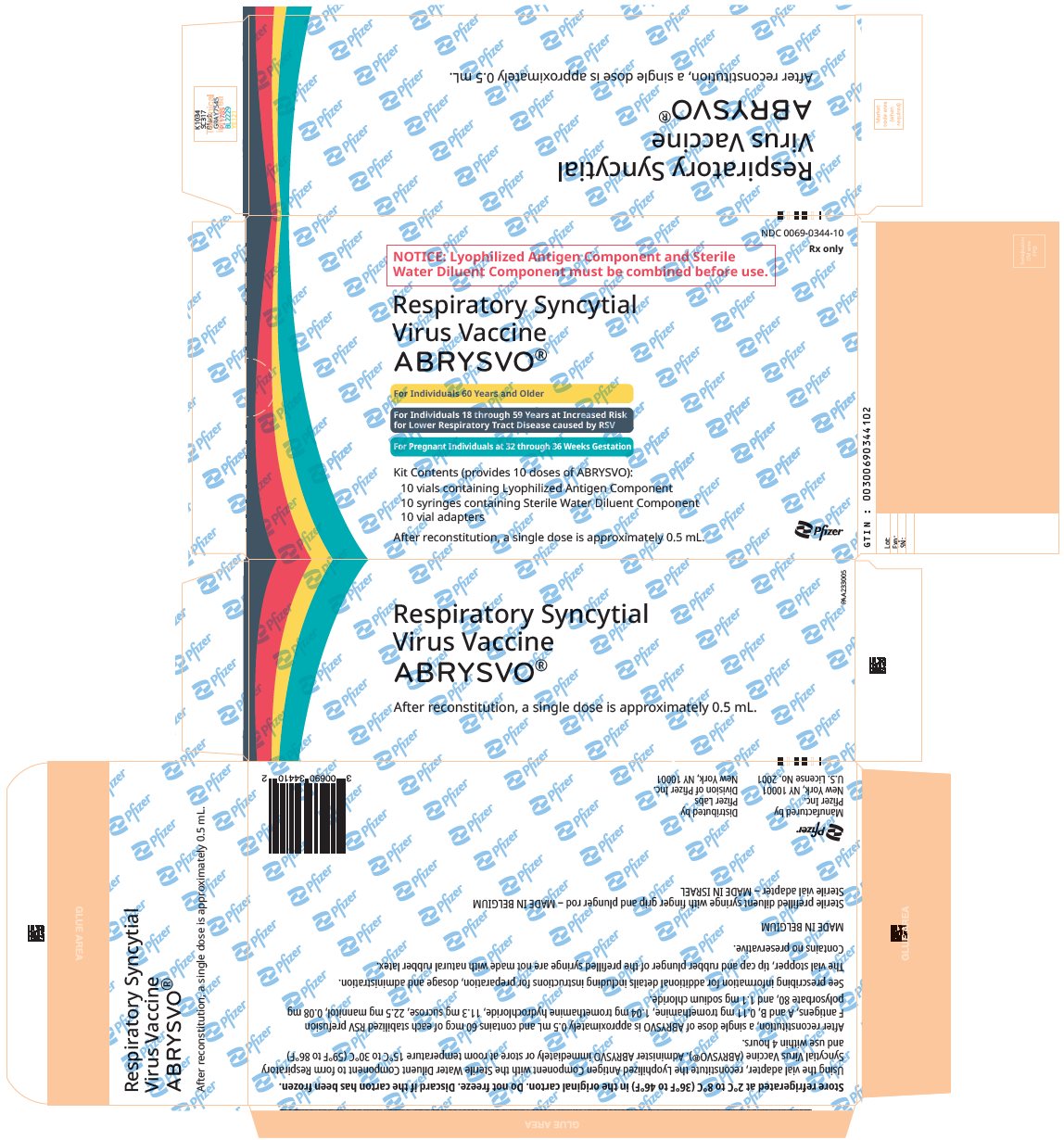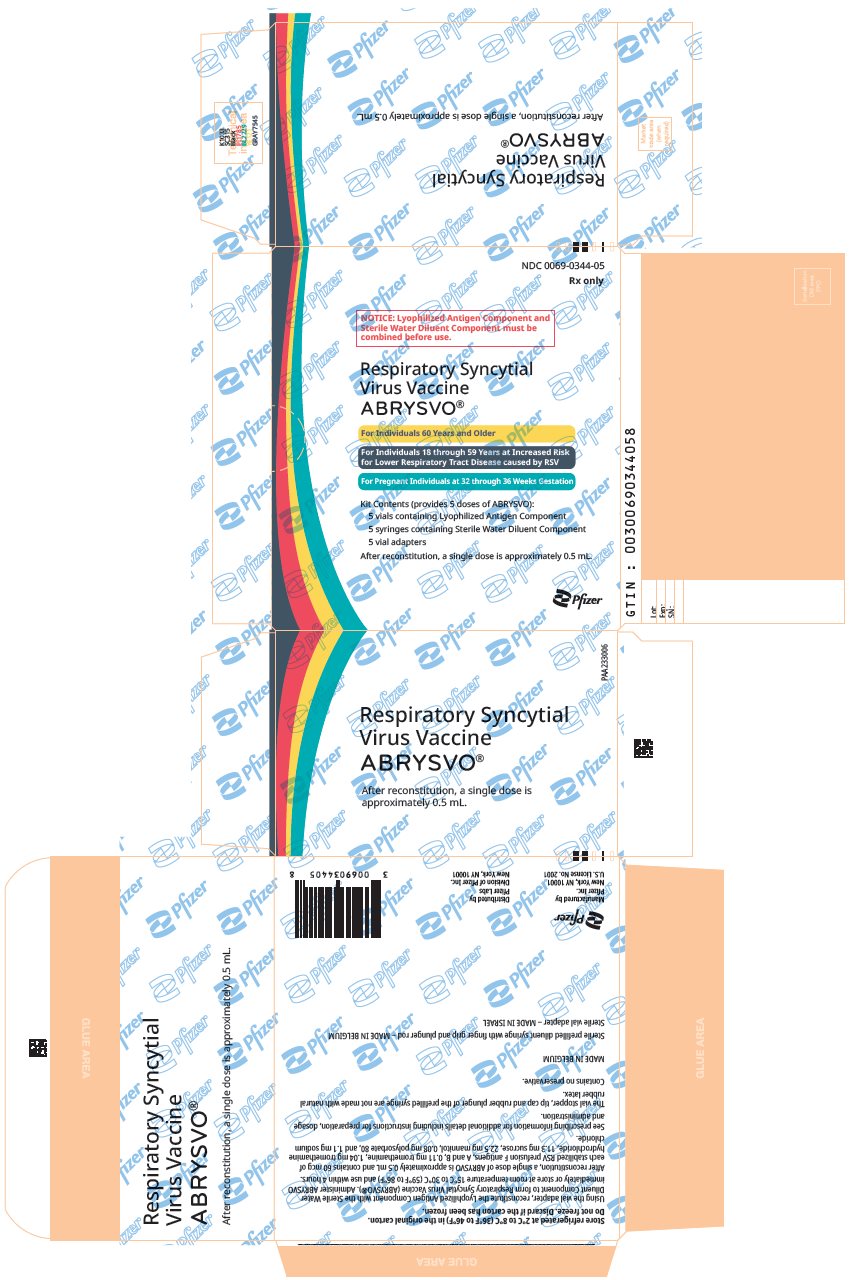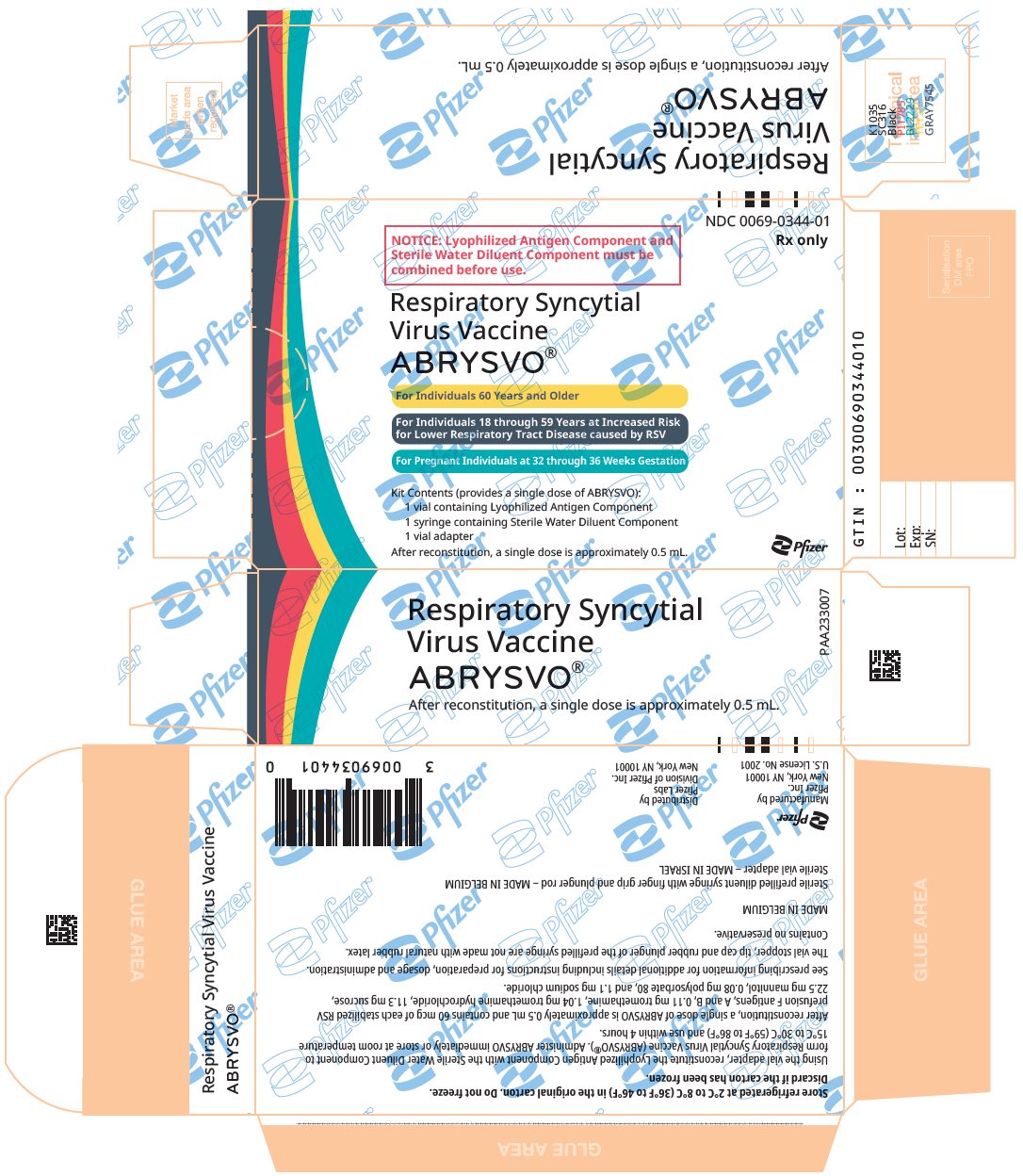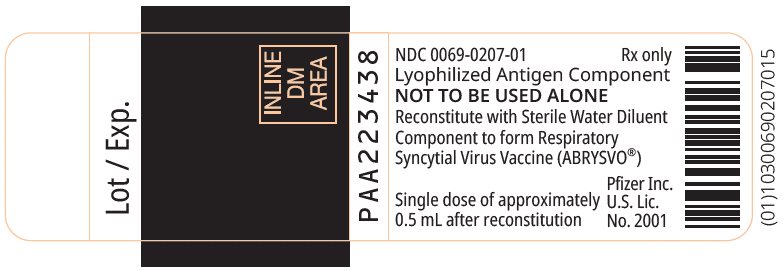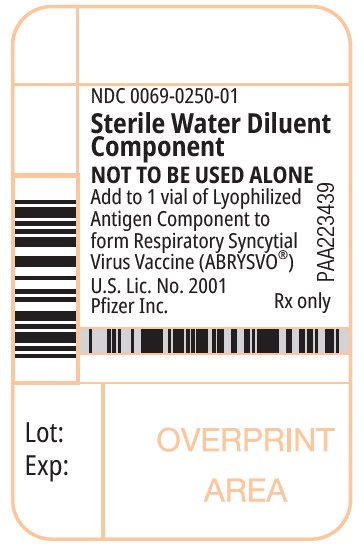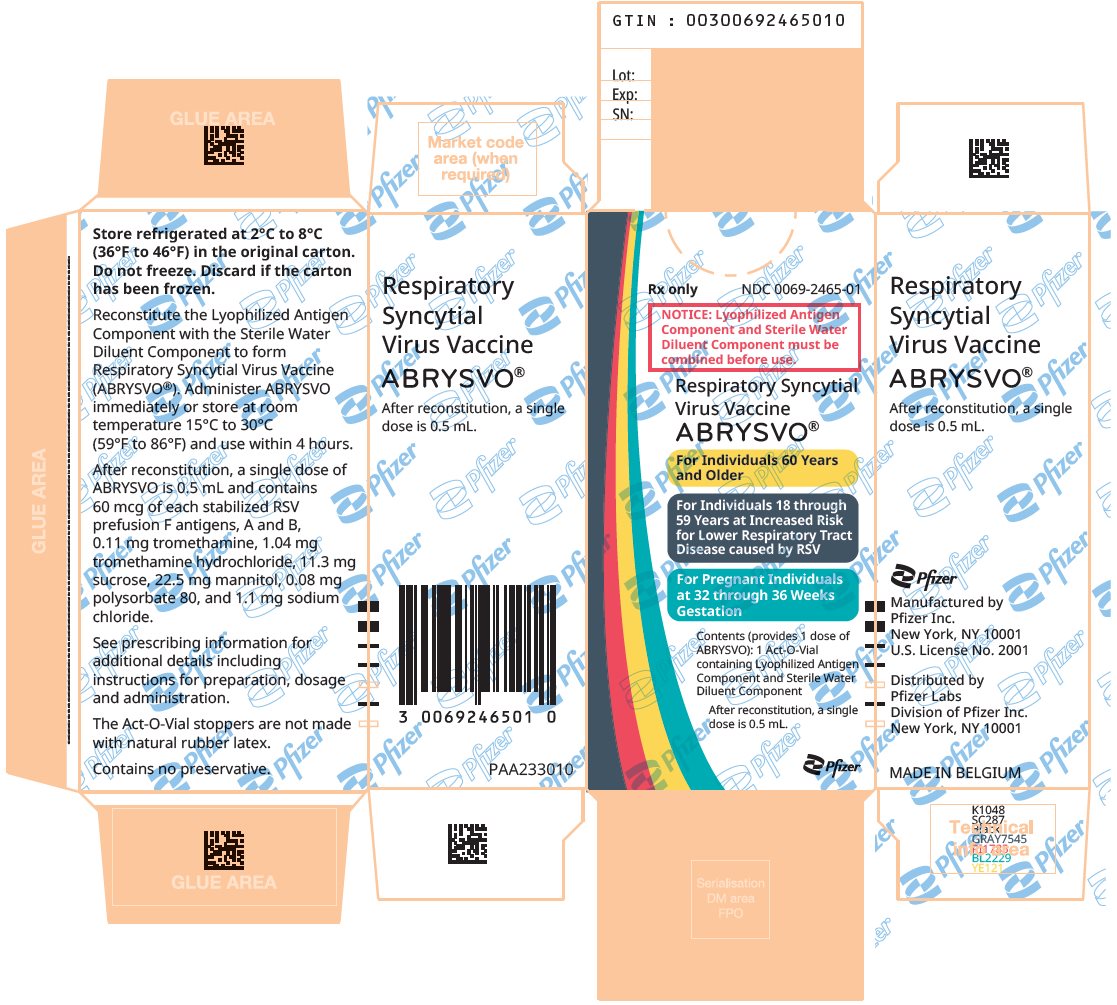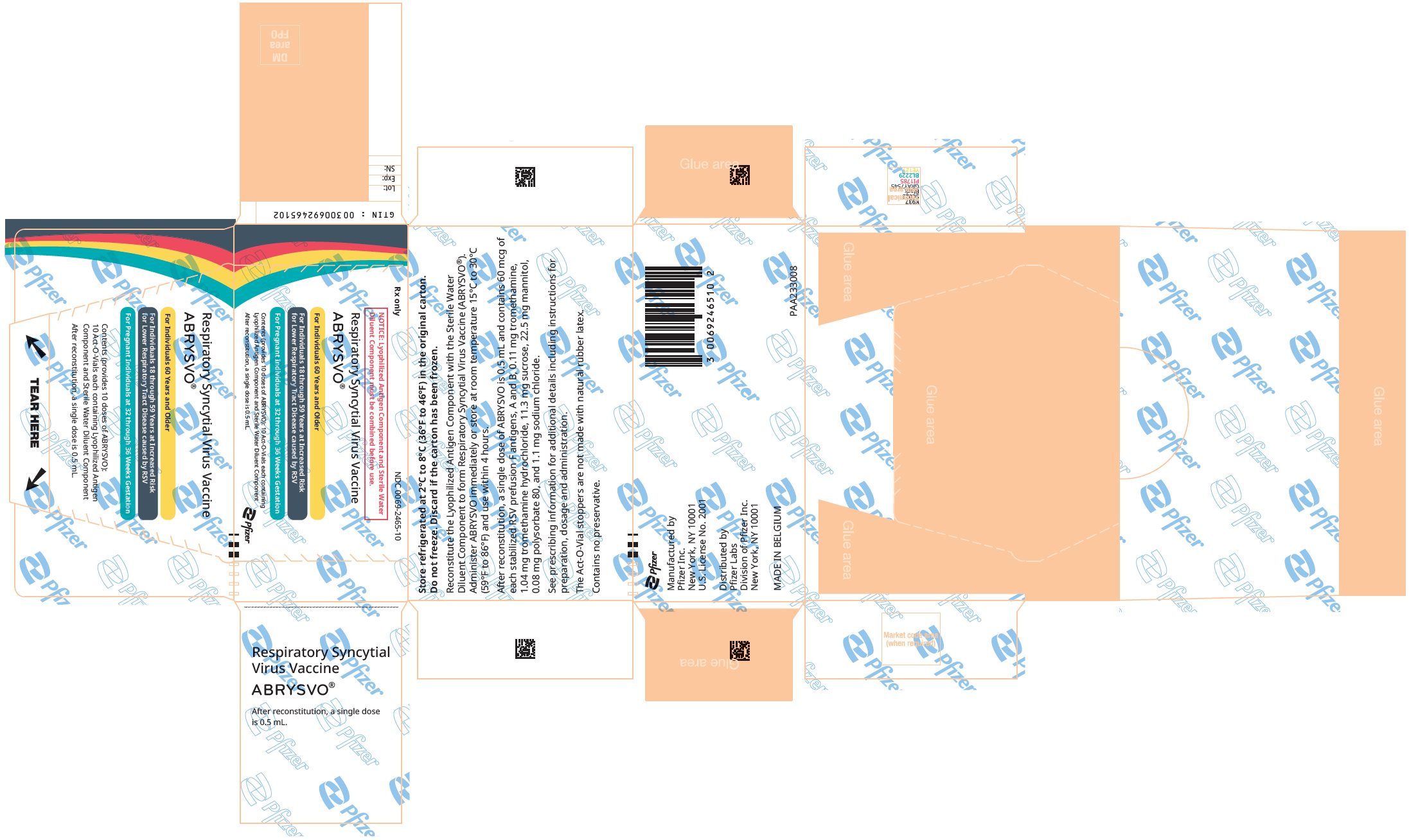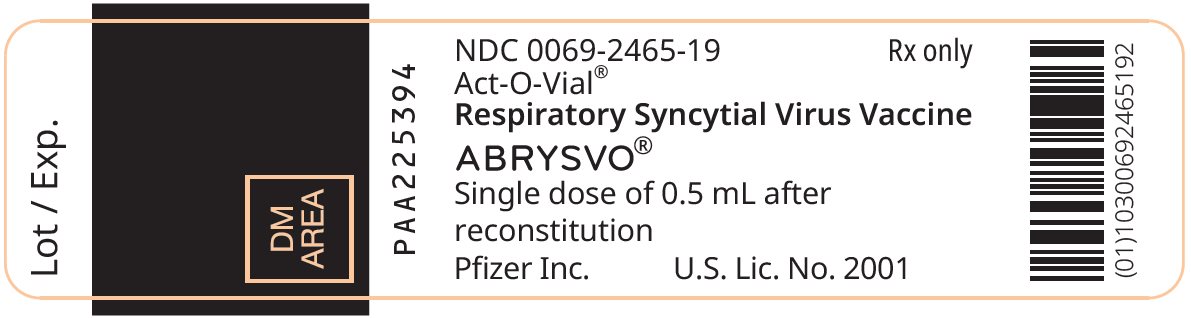 DRUG LABEL: Abrysvo
NDC: 0069-0344 | Form: KIT | Route: INTRAMUSCULAR
Manufacturer: Pfizer Laboratories Div Pfizer Inc
Category: other | Type: VACCINE LABEL
Date: 20251223

ACTIVE INGREDIENTS: RECOMBINANT STABILIZED RSV A PREFUSION F ANTIGEN 0.06 mg/0.5 mL; RECOMBINANT STABILIZED RSV B PREFUSION F ANTIGEN 0.06 mg/0.5 mL
INACTIVE INGREDIENTS: TROMETHAMINE 0.11 mg/0.5 mL; TROMETHAMINE HYDROCHLORIDE 1.04 mg/0.5 mL; SUCROSE 11.3 mg/0.5 mL; MANNITOL 22.5 mg/0.5 mL; POLYSORBATE 80 0.08 mg/0.5 mL; SODIUM CHLORIDE 1.1 mg/0.5 mL; WATER

HIGHLIGHTS OF PRESCRIBING INFORMATION

These highlights do not include all the information needed to use ABRYSVO safely and effectively. See full prescribing information for ABRYSVO.
ABRYSVO® (Respiratory Syncytial Virus Vaccine) for injection, for intramuscular use
Initial U.S. Approval: 2023

RECENT MAJOR CHANGES

Warnings and Precautions, Guillain‑Barré Syndrome (5.1) | 1/2025

1 INDICATIONS AND USAGE

ABRYSVO is a vaccine indicated for

- Active immunization of pregnant individuals at 32 through 36 weeks gestational age for the prevention of lower respiratory tract disease (LRTD) and severe LRTD caused by respiratory syncytial virus (RSV) in infants from birth through 6 months of age. (1.1)
- Active immunization for the prevention of LRTD caused by RSV in individuals 60 years of age and older. (1.2)
- Active immunization for the prevention of LRTD caused by RSV in individuals 18 through 59 years of age who are at increased risk for LRTD caused by RSV. (1.3)

2 DOSAGE AND ADMINISTRATION

- For intramuscular use. (2)
- After reconstitution, a single dose of ABRYSVO is either 0.5 mL (Act-O-Vial® presentation and vial and vial presentation) or approximately 0.5 mL (vial and prefilled syringe presentation). (2.1)

3 DOSAGE FORMS AND STRENGTHS

For injection.

- For the Act-O-Vial presentation, a single dose after reconstitution is 0.5 mL. (3)
- For the vial and prefilled syringe presentation, a single dose after reconstitution is approximately 0.5 mL. (3)
- For the vial and vial presentation, a single dose after reconstitution is 0.5 mL. (3)

4 CONTRAINDICATIONS

History of severe allergic reaction (e.g., anaphylaxis) to any component of ABRYSVO. (4)

5 WARNINGS AND PRECAUTIONS

- Guillain‑Barré Syndrome. The results of a postmarketing observational study suggest an increased risk of Guillain‑Barré syndrome during the 42 days following vaccination with ABRYSVO. (5.1, 6.2)
- Potential risk of preterm birth. To avoid the potential risk of preterm birth with use of ABRYSVO before 32 weeks of gestation, administer ABRYSVO as indicated in pregnant individuals at 32 through 36 weeks gestational age. (5.2)

6 ADVERSE REACTIONS

- The most commonly reported solicited local and systemic adverse reactions in pregnant individuals (≥10%) were pain at the injection site (40.6%), headache (31.0%), muscle pain (26.5%), and nausea (20.0%). (6.1)
- The most commonly reported solicited local and systemic adverse reactions in individuals 60 years of age and older (≥10%) were fatigue (15.7%), headache (12.9%), pain at the injection site (10.6%), and muscle pain (10.2%). (6.1)
- The most commonly reported solicited local and systemic adverse reactions in individuals 18 through 59 years of age (≥10%) were pain at the injection site (35.3%), muscle pain (24.4%), joint pain (12.4%), and nausea (11.8%). (6.1)

To report SUSPECTED ADVERSE REACTIONS, contact Pfizer Inc. at 1-800-438-1985 or VAERS at 1-800-822-7967 or http://vaers.hhs.gov.

FULL PRESCRIBING INFORMATION

1 INDICATIONS AND USAGE

1.1 Immunization of Pregnant Individuals

ABRYSVO is a vaccine indicated for active immunization of pregnant individuals at 32 through 36 weeks gestational age for the prevention of lower respiratory tract disease (LRTD) and severe LRTD caused by respiratory syncytial virus (RSV) in infants from birth through 6 months of age.

1.2 Immunization of Individuals 60 Years of Age and Older

ABRYSVO is a vaccine indicated for active immunization for the prevention of LRTD caused by RSV in individuals 60 years of age and older.

1.3 Immunization of Individuals 18 Through 59 Years of Age

ABRYSVO is a vaccine indicated for active immunization for the prevention of LRTD caused by RSV in individuals 18 through 59 years of age who are at increased risk for LRTD caused by RSV.

2 DOSAGE AND ADMINISTRATION

2.1 Dose and Schedule

After reconstitution, a single dose of ABRYSVO is either 0.5 mL (Act-O-Vial presentation and vial and vial presentation) or approximately 0.5 mL (vial and prefilled syringe presentation) [see Dosage and Administration (2.2)].

2.2 Presentations and Reconstitution

ABRYSVO is supplied in 3 presentations as follows:

Act-O-Vial Presentation

The Act-O-Vial presentation is supplied in cartons. Each Act-O-Vial contains the Lyophilized Antigen Component (a sterile white powder) and Sterile Water Diluent Component.

Vial and Prefilled Syringe Presentation

The vial and prefilled syringe presentation is supplied in cartons containing a kit(s). Each kit includes a vial of Lyophilized Antigen Component (a sterile white powder), a prefilled syringe containing Sterile Water Diluent Component, and a vial adapter.

Vial and Vial Presentation

The vial and vial presentation is supplied in cartons that include vials of Lyophilized Antigen Component (a sterile white powder) and vials containing Sterile Water Diluent Component.

For all presentations, reconstitute the Lyophilized Antigen Component with the Sterile Water Diluent Component to form ABRYSVO, as described in the instructions below.

Reconstitution Instructions for the Act-O-Vial Presentation

Act-O-Vial presentation

Step 1. Reconstitution of the Lyophilized Antigen Component with the Sterile Water Diluent Component to form ABRYSVO
Place the Act-O-Vial on a flat surface and firmly press down on the plastic activator cap to release the center stopper and Sterile Water Diluent Component into the lower chamber.
Gently swirl the Act-O-Vial until the powder is completely dissolved.
Do not shake.

Step 2. Withdrawal of ABRYSVO
Remove the plastic tab covering the center of the top stopper.
Using a sterile needle and syringe, insert the needle straight through the center of the stopper.
Invert the Act-O-Vial and withdraw 0.5 mL of ABRYSVO.
Discard the Act-O-Vial and excess volume after withdrawal of a single dose.

Reconstitution Instructions for Vial and Prefilled Syringe Presentation

Step 1. Attachment of the vial adapter to the vial
Remove the flip top cap from the vial of Lyophilized Antigen Component.
Peel off the top cover from the vial adapter packaging.
While keeping the vial adapter in its packaging, center the adapter over the vial’s stopper and attach to the vial with a straight downward push.
Remove the packaging.

Step 2. Connection of the syringe to the vial adapter
Hold the syringe of Sterile Water Diluent Component by the Luer lock adapter.
Twist to remove the syringe cap.
Connect the syringe to the vial adapter by turning the Luer lock.

Step 3. Reconstitution of the Lyophilized Antigen Component with the Sterile Water Diluent Component to form ABRYSVO
Inject the entire contents of the syringe into the vial.
Hold the plunger rod down and gently swirl the vial until the powder is completely dissolved.
Do not shake.

Step 4. Withdrawal of ABRYSVO
Invert the vial completely and slowly withdraw the entire contents into the syringe for an approximately 0.5 mL dose of ABRYSVO.
Twist to disconnect the syringe from the vial adapter.
Attach a sterile needle suitable for intramuscular use.

Reconstitution Instructions for the Vial and Vial Presentation

Step 1. Withdrawal of the Sterile Water Diluent
Using a sterile needle and sterile syringe, withdraw the entire contents of the vial containing the Sterile Water Diluent Component.

Step 2. Reconstitution of the Lyophilized Antigen Component with the Sterile Water Diluent Component to form ABRYSVO
Inject the entire contents into the vial containing the Lyophilized Antigen Component (white powder). Gently swirl the vial in a circular motion until the powder is completely dissolved. Do not shake.

Step 3. Withdrawal of ABRYSVO
Withdraw 0.5 mL from the vial containing the reconstituted vaccine.
Discard the vial and any excess volume after withdrawal of a single dose.

2.3 Administration

For intramuscular use.

After reconstitution, ABRYSVO is a clear and colorless solution. Parenteral drug products should be inspected visually for particulate matter and discoloration prior to administration, whenever solution and container permit. Discard if either condition is present.

Administer ABRYSVO immediately or store at room temperature [15°C to 30°C (59°F to 86°F)] and use within 4 hours. Discard reconstituted vaccine if not used within 4 hours.

3 DOSAGE FORMS AND STRENGTHS

For injection.

For the Act-O-Vial presentation, a single dose after reconstitution is 0.5 mL.

For the vial and prefilled syringe presentation, a single dose after reconstitution is approximately 0.5 mL.

For the vial and vial presentation, a single dose after reconstitution is 0.5 mL.

4 CONTRAINDICATIONS

Do not administer ABRYSVO to individuals with a history of a severe allergic reaction (e.g., anaphylaxis) to any component of ABRYSVO [see Description (11)].

5 WARNINGS AND PRECAUTIONS

5.1 Guillain-Barré Syndrome

The results of a postmarketing observational study suggest an increased risk of Guillain‑Barré syndrome (GBS) during the 42 days following vaccination with ABRYSVO [see Adverse Reactions (6.2)].

5.2 Potential Risk of Preterm Birth

A numerical imbalance in preterm births in ABRYSVO recipients was observed compared to placebo recipients in two clinical studies [see Adverse Reactions (6.1)]. Available data are insufficient to establish or exclude a causal relationship between preterm birth and ABRYSVO. To avoid the potential risk of preterm birth with use of ABRYSVO before 32 weeks of gestation, administer ABRYSVO as indicated in pregnant individuals at 32 through 36 weeks gestational age. Pregnant individuals who were at increased risk of preterm birth were generally excluded from clinical studies of ABRYSVO.

5.3 Management of Acute Allergic Reactions

Appropriate medical treatment used to manage immediate allergic reactions must be immediately available in the event an anaphylactic reaction occurs following administration of ABRYSVO.

5.4 Syncope

Syncope (fainting) may occur in association with administration of injectable vaccines, including ABRYSVO. Procedures should be in place to avoid injury from fainting.

5.5 Altered Immunocompetence

Immunocompromised individuals, including those receiving immunosuppressive therapy, may have a diminished immune response to ABRYSVO.

5.6 Limitations of Vaccine Effectiveness

Vaccination with ABRYSVO may not protect all vaccine recipients.

6 ADVERSE REACTIONS

In pregnant individuals, the most commonly reported (≥10%) adverse reactions were pain at the injection site (40.6%), headache (31.0%), muscle pain (26.5%), and nausea (20.0%).

In individuals 60 years of age and older, the most commonly reported (≥10%) adverse reactions were fatigue (15.7%), headache (12.9%), pain at the injection site (10.6%), and muscle pain (10.2%).

In individuals 18 through 59 years of age with chronic medical conditions, the most commonly reported (≥10%) adverse reactions and for which the rate for ABRYSVO exceeds the rate for placebo were pain at the injection site (35.3%), muscle pain (24.4%), joint pain (12.4%), and nausea (11.8%).

6.1 Clinical Trials Experience

Because clinical trials are conducted under widely varying conditions, adverse reaction rates observed in the clinical trials of a vaccine cannot be directly compared to rates in the clinical trials of another vaccine and may not reflect the rates observed in practice.

Pregnant Individuals and Infants from Birth Through 6 Months of Age

The safety of ABRYSVO in maternal and infant participants was evaluated in two clinical studies in which approximately 4,000 maternal participants received a single dose of ABRYSVO.

Study 1 (NCT04424316) was a Phase 3, randomized, double-blind, multicenter, placebo-controlled study to investigate the efficacy and safety of ABRYSVO administered to pregnant individuals ≤49 years of age with uncomplicated, singleton pregnancies, to protect their infants against RSV disease. Pregnant individuals with high-risk pregnancies were excluded from the study (BMI>40 kg/m^2 prior to pregnancy, pregnancies resulting after in vitro fertilization, preeclampsia, eclampsia, uncontrolled gestational hypertension, placental abnormalities, polyhydramnios or oligohydramnios, significant bleeding or blood clotting disorder, unstable endocrine disorders including untreated disorders of glucose intolerance or thyroid disorders). Pregnant individuals with prior pregnancy complications (e.g., history of preterm birth ≤34 weeks gestation, prior stillbirth, neonatal death, previous infant with a known genetic disorder or significant congenital anomaly) could be included, based on the investigators’ judgment, but were generally not enrolled in the study. In this study with 1:1 randomization 3,698 participants received ABRYSVO and 3,687 received placebo (0.5 mL dose, containing the same buffer ingredients in the same quantities as in a single dose of ABRYSVO [see Description (11)]). Infants born in year 1 were followed for up to 24 months, and infants born in year 2 were followed for up to 12 months to assess safety. At the time of final data evaluation, 3,659 infants were born to the maternal participants in the ABRYSVO group and 3,646 in the placebo group, and of these, approximately 93.3% have been followed for 12 months and 86.7% for 24 months. This multicenter study was conducted in Argentina, Australia, Brazil, Canada, Chile, Denmark, Finland, Gambia, Japan, Republic of Korea, Mexico, Netherlands, New Zealand, Philippines, South Africa, Spain, Taiwan, and the US.

Demographic characteristics in Study 1 among participants who received ABRYSVO and those who received placebo were generally similar with regard to age, race, and ethnicity. Of the participants in the study, 65% were White, 20% were Black or African American, 13% were Asian, and 29% were Hispanic/Latino. The median maternal age at the time of study vaccination was 29 years (range 16 to 45 years in the ABRYSVO group, 14 to 47 years in the placebo group). The median gestational age at vaccination was 31 weeks and 2 days (range 24-36.9 weeks). ABRYSVO is approved for use for pregnant individuals at 32 through 36 weeks gestational age [see Indications and Usage (1.1)]. The median infant gestational age at birth was 39 weeks and 1 day (range 27 weeks and 3 days to 44 weeks and 2 days). Among the infants born to maternal participants 51% were male and 49% were female.

Study 2 (NCT04032093) was a Phase 2, randomized, placebo-controlled, observer-blinded study that investigated the safety of two dose levels (120 mcg and a higher dose) of ABRYSVO administered to pregnant individuals. ABRYSVO (120 mcg) was administered to 115 maternal participants, and 114 infants were born to these maternal participants. This study was conducted in the US, South Africa, Argentina, and Chile. Demographic characteristics among participants who received ABRYSVO and those who received placebo were generally similar with regard to age, race, and ethnicity. Of the participants in the study, 76% were White, 21% were Black or African American, and 28% were Hispanic/Latino. The median age of participants was 27 years (range 18-42 years). The median gestational age at vaccination was 30 weeks (range 24-36 weeks). ABRYSVO is approved for use for pregnant individuals at 32 through 36 weeks gestational age [see Indications and Usage (1.1)].

For all maternal participants in Study 1, solicited local reactions and systemic events were collected using electronic diaries for 7 days after study vaccination, adverse events for 1 month and obstetric complications, serious adverse events, and adverse events of special interest for the duration of the study. For infant participants, the collection period for nonserious adverse events was from birth to 1 month. Serious adverse events were monitored for at least 1 year for all infant participants and for up to 2 years for half of the infants in Study 1.

Solicited Local and Systemic Reactions in Study 1

The majority of solicited local and systemic reactions in maternal participants resolved within 2-3 days of onset. Severe local reactions were reported for 0.3% of maternal participants in the ABRYSVO group and none in the placebo group, and severe systemic reactions within 7 days after vaccination were reported by 2.3% of maternal participants in both groups.

Solicited local and systemic reactions reported within 7 days after vaccination in Study 1 are presented in Tables 1 and 2.

Table 1 Percentage of Maternal Participants with Local Reactions Reported, by Maximum Severity, within 7 Days after Vaccination – Study 1 [NCT04424316]
Local Reactions | ABRYSVO; N=3,663 [N = number of participants who provided e-diary data for a specific reaction after vaccination.]; % | PLACEBO; N=3,639; %
Injection site pain [Mild: does not interfere with activity; moderate: interferes with activity; severe: prevents daily activity.]
Any [Any includes all participants who reported a reaction as mild, moderate, or severe during Day 1 to Day 7 after vaccination.] | 40.6 | 10.1
Mild | 36.1 | 9.3
Moderate | 4.4 | 0.9
Severe | 0.1 | 0
Redness [Mild: >2 cm to 5 cm; moderate: >5 cm to 10 cm; severe: >10 cm.]
Any | 7.2 | 0.2
Mild | 5.0 | 0.1
Moderate | 2.1 | 0.1
Severe | 0.1 | 0
Swelling
Any | 6.2 | 0.2
Mild | 4.1 | 0.1
Moderate | 2.0 | <0.1
Severe | <0.1 | 0
Note: The presented results are based on the participants with solicited local reactogenicity data at the time of the data cut-off date for the primary analysis.

Table 2 Percentage of Maternal Participants with Systemic Reactions Reported, by Maximum Severity, within 7 Days after Vaccination – Study 1 [NCT04424316]
Systemic Reactions | ABRYSVO; N=3,663 [N = number of participants who provided e-diary data for a specific reaction after vaccination.]; % | PLACEBO; N=3,638-3,639; %
Fever (≥38.0℃)
≥38.0°C | 2.6 | 2.9
≥38.0°C to 38.4°C | 1.7 | 1.5
>38.5°C to 38.9°C | 0.8 | 1.2
>39.0°C to 40.0°C | <0.1 | 0.1
>40.0°C | <0.1 | 0.1
Fatigue [Mild: does not interfere with activity; moderate: some interference with activity; severe: prevents daily routine activity.]
Any [Any includes all participants who reported a reaction as mild, moderate, or severe during Day 1 to Day 7 after vaccination.] | 46.1 | 43.8
Mild | 23.4 | 22.8
Moderate | 21.4 | 19.6
Severe | 1.3 | 1.4
Headache
Any | 31.0 | 27.6
Mild | 20.2 | 17.9
Moderate | 10.4 | 9.3
Severe | 0.4 | 0.4
Muscle pain
Any | 26.5 | 17.1
Mild | 17.6 | 10.0
Moderate | 8.6 | 6.8
Severe | 0.4 | 0.3
Nausea
Any | 20.0 | 19.2
Mild | 14.4 | 13.8
Moderate | 5.4 | 5.2
Severe | 0.2 | 0.2
Joint pain
Any | 11.6 | 10.5
Mild | 6.5 | 6.0
Moderate | 4.9 | 4.4
Severe | 0.2 | <0.1
Diarrhea [Mild: 2 to 3 loose stools in 24 hours; moderate: 4 to 5 loose stools in 24 hours; severe: 6 or more loose stools in 24 hours.]
Any | 11.2 | 11.5
Mild | 9.1 | 9.4
Moderate | 2.0 | 1.9
Severe | 0.1 | 0.2
Vomiting [Mild: 1 to 2 times in 24 hours; moderate: >2 times in 24 hours; severe: requires intravenous hydration.]
Any | 7.8 | 7.0
Mild | 6.4 | 5.4
Moderate | 1.3 | 1.5
Severe | 0.2 | <0.1
Note: The presented results are based on the participants with solicited systemic reactogenicity data at the time of the data cut-off date for the primary analysis.

Unsolicited Adverse Events in Study 1

Unsolicited adverse events reported within 1 month after vaccination by maternal participants were 14.0% in the ABRYSVO group and 13.2% in the placebo group.

The most frequently reported unsolicited adverse events in maternal participants from vaccination through the 1-month follow-up visit were disorders of pregnancy, puerperium and perinatal conditions (7.1% for the ABRYSVO group versus 6.3% for the placebo group).

Within 14 days of vaccination, lymphadenopathy was reported in 2 vaccine recipients and 0 placebo recipients and was considered related to ABRYSVO.

Serious Adverse Events in Study 1

In Study 1, serious adverse events in maternal participants were reported by 16.6% in the ABRYSVO group and 15.8% in the placebo group occurring any time during the study (see Table 3) with 4.3% serious adverse events in the ABRYSVO group and 3.8% in the placebo group occurring within 1 month after vaccination. Most of the serious adverse events in maternal participants were related to pregnancy complications and occurred after the 1 month period following vaccination.

Table 3 Select Pregnancy-related Serious Adverse Events in Study 1 in Pregnant Individuals Occurring at any Time Following Vaccination [Includes all SAEs from vaccination to 6 months post-delivery (up to approximately 10 months, depending on the gestational age at the time of vaccination). In Study 1, HELLP syndrome occurred in 5 participants (2 in the ABRYSVO group and 3 in the placebo group).]
Serious Adverse Reaction | ABRYSVO; N=3,698; n (%) | 95% CI | Placebo; N=3,687; n (%) | 95% CI
All Maternal SAEs | 613 (16.6) | (15.4, 17.8) | 581 (15.8) | (14.6, 17.0)
Pre-eclampsia | 67 (1.8) | (1.4, 2.3) | 53 (1.4) | (1.1, 1.9)
Gestational hypertension | 43 (1.2) | (0.8, 1.6) | 41 (1.1) | (0.8, 1.5)
Eclampsia | 7 (0.2) | (0.1, 0.4) | 3 (<0.1) | (0.0, 0.2)
Premature rupture of membranes | 14 (0.4) | (0.2, 0.6) | 16 (0.4) | (0.2, 0.7)
Preterm premature rupture of membranes | 15 (0.4) | (0.2, 0.7) | 11 (0.3) | (0.1, 0.5)
Hypertension | 13 (0.4) | (0.2, 0.6) | 6 (0.2) | (0.1, 0.4)
Maternal death [There was one maternal death in the ABRYSVO group due to postpartum hemorrhage that was not likely to be associated with vaccination.] | 1 (<0.1) | (0.0, 0.2) | 0 | (0.0, 0.1)
Fetal death [A total of 19 intrauterine deaths were reported for the index pregnancy: 10 intrauterine deaths in the ABRYSVO group (0.3%) and 9 intrauterine deaths in the placebo group (0.2%). The intrauterine deaths represented various clinical conditions and presentations resulting in fetal demise without clear evidence of a common pathophysiology.] | 10 (0.3) | (0.1, 0.5) | 9 (0.2) | (0.1, 0.5)

Preterm Births in Study 1 and Study 2

A numerical imbalance in preterm births in ABRYSVO recipients compared to placebo recipients was observed in both Studies 1 and 2. In Study 2, preterm births occurred in 5.3% (6 out of 114) in the ABRYSVO group and 2.6% (3 out of 116) in the placebo group. In the subsequent Study 1, preterm birth events occurred in 5.7% [95% CI: 4.9, 6.5] (207 out of 3,659) in the ABRYSVO group and 4.7% [95% CI: 4.1, 5.5] (172 out of 3,646) in the placebo group. In infants born preterm, 84 infants in the ABRYSVO group and 81 infants in the placebo group remained hospitalized or were readmitted to the hospital in the neonatal period (up to 30 days after birth). Available data are insufficient to establish or exclude a causal relationship between preterm birth and ABRYSVO.

A numerical imbalance in preterm births was also observed in Study 1 among the subgroup of infants born to participants who were vaccinated at 32 through 36 weeks gestation, with 4.3% (71/1,667) in the ABRYSVO group and 3.7% (60/1,640) in the placebo group.

Adverse Reactions in Infants

In Study 1, adverse events in infants from birth to 1 month of age were observed in 38.0% in the ABRYSVO group compared to 35.4% in the placebo group. Low birth weight was observed in 5.1% of participants in the ABRYSVO group versus 4.3% in the placebo group, and neonatal jaundice was observed in 7.3% in the ABRYSVO group versus 6.9% in the placebo group.

Individuals 18 Years of Age and Older

Individuals 60 Years of Age and Older

The safety of ABRYSVO was evaluated in Study 3 (NCT05035212) in which 18,574 participants received ABRYSVO and 18,288 received placebo (0.5 mL dose, containing the same buffer ingredients in the same quantities as in a single dose of ABRYSVO [see Description (11)]). Study 3 was a multicenter, randomized, double-blind, placebo-controlled study to assess the efficacy and safety of ABRYSVO in individuals 60 years of age and older. This study was conducted in the US, Argentina, Japan, the Netherlands, Canada, South Africa, and Finland. Demographic characteristics among participants who received ABRYSVO and those who received placebo were generally similar with regard to age, sex, race, and ethnicity. Of the participants in the study, 51% were male and 80% were White, 12% were Black or African American, 7% were Asian, and 41% were Hispanic/Latino. The median age of participants was 67 years (range 59-97 years).

Solicited local and systemic reactions were collected using electronic diaries for 7 days after study vaccination in 7,116 participants (3,669 ABRYSVO participants and 3,447 placebo recipients) from a subset of sites. For all participants, unsolicited adverse events were collected for one month after study vaccination; serious adverse events (SAEs) are collected throughout study participation with a median duration of follow-up of 17.5 months.

Solicited Local and Systemic Reactions in Study 3

Solicited local and systemic reactions reported within 7 days after vaccination in Study 3 are presented in Tables 4 and 5.

Table 4 Percentage of Participants 60 Years of Age and Older with Local Reactions Reported, by Maximum Severity, within 7 Days after Vaccination – Study 3 [NCT05035212]
Local Reactions | ABRYSVO N=3,628 [N = number of participants who provided e-diary data for a specific reaction after vaccination.] % | PLACEBO N=3,447 %
Injection site pain [Mild: does not interfere with activity; moderate: some interference with activity; severe: prevents daily activity.]
Any [Any includes all participants who reported a reaction as mild, moderate, or severe during Day 1 to Day 7 after vaccination.] | 10.6 | 6.1
Mild | 9.5 | 5.4
Moderate | 1.1 | 0.7
Severe | <0.1 | 0
Redness [Mild: 2.5 cm to 5 cm; moderate: >5 cm to 10 cm; severe: >10 cm (for data reported from e-diaries).]
Any | 2.7 | 0.6
Mild | 1.6 | 0.4
Moderate | 1.0 | 0.2
Severe | 0.1 | 0
Swelling
Any | 2.5 | 0.4
Mild | 1.5 | 0.2
Moderate | 0.9 | 0.1
Severe | 0.1 | <0.1

Table 5 Percentage of Participants 60 Years of Age and Older with Systemic Reactions Reported, by Maximum Severity, within 7 Days after Vaccination – Study 3 [NCT05035212]
Systemic Reactions | ABRYSVO N=3,628 [N = number of participants who provided e-diary data for a specific reaction after vaccination.] % | PLACEBO N=3,447 %
Fever (≥38.0℃)
≥38.0°C | 1.4 | 1.5
≥38.0°C to 38.4°C | 0.6 | 0.8
>38.4°C to 38.9°C | 0.8 | 0.6
>38.9°C to 40.0°C | <0.1 | <0.1
>40.0°C | 0 | <0.1
Fatigue [Mild: does not interfere with activity; moderate: some interference with activity; severe: prevents daily routine activity.]
Any [Any includes all participants who reported a reaction as mild, moderate, or severe during Day 1 to Day 7 after vaccination.] | 15.7 | 14.8
Mild | 9.3 | 8.6
Moderate | 6.0 | 6.0
Severe | 0.3 | 0.1
Headache
Any | 12.9 | 12.0
Mild | 9.0 | 8.6
Moderate | 3.8 | 3.2
Severe | 0.1 | <0.1
Muscle pain
Any | 10.2 | 8.5
Mild | 6.5 | 5.6
Moderate | 3.5 | 2.8
Severe | 0.2 | <0.1
Joint pain
Any | 7.6 | 7.0
Mild | 4.5 | 3.9
Moderate | 3.0 | 3.0
Severe | <0.1 | <0.1
Nausea
Any | 3.5 | 3.8
Mild | 2.6 | 3.1
Moderate | 0.9 | 0.6
Severe | 0 | <0.1
Vomiting [Mild: 1 to 2 times in 24 hours; moderate: >2 times in 24 hours; severe: requires intravenous hydration.]
Any | 0.9 | 0.9
Mild | 0.7 | 0.7
Moderate | 0.2 | 0.2
Severe | 0 | <0.1
Diarrhea [Mild: 2 to 3 loose stools in 24 hours; moderate: 4 to 5 loose stools in 24 hours; severe: 6 or more loose stools in 24 hours.]
Any | 6.0 | 5.3
Mild | 4.5 | 4.3
Moderate | 1.4 | 0.9
Severe | 0.1 | 0.1

Solicited local and systemic reactions had a median duration of 1-2 days.

Unsolicited Adverse Events in Study 3

Unsolicited adverse events occurring within 1 month after vaccination were similar between groups, reported in 10.8% and 10.5% of participants who received ABRYSVO and placebo, respectively.

Within 30 days after vaccination, atrial fibrillation was reported in 11 vaccine recipients and 3 placebo recipients (of which 5 in the ABRYSVO group and 2 in the placebo group were serious adverse events); the onset of symptoms was 18 to 30 days post vaccination. The currently available information on atrial fibrillation is insufficient to determine a causal relationship to the vaccine [see Use in Specific Populations (8.6)]. Within 14 days of vaccination, lymphadenopathy was reported in 6 vaccine recipients, considered related to ABRYSVO, and 3 placebo recipients. There were no other notable patterns or numerical imbalances between groups for specific categories of unsolicited adverse events.

Serious Adverse Events in Study 3

In Study 3, SAEs were reported by 6.2% of participants in the ABRYSVO group and 6.1% in the placebo group. Three participants in the ABRYSVO group had SAEs which were assessed as possibly related to study vaccination: Guillain‑Barré syndrome reported 7 days after vaccination (with diagnosis later revised to chronic inflammatory demyelinating polyneuropathy), Miller Fisher syndrome reported 8 days after vaccination, and hypersensitivity reported 8 hours after vaccination.

Individuals 18 through 59 Years of Age Considered to be at Increased Risk of LRTD caused by RSV

The safety of ABRYSVO was evaluated in Study 4 Substudy A (NCT05842967) in which 453 participants received ABRYSVO and 225 received placebo (0.5 mL dose, containing the same buffer ingredients in the same quantities as in a single dose of ABRYSVO [see Description (11)]). Study 4 was a multicenter, randomized, double-blind, placebo-controlled study to assess the safety and immunogenicity of ABRYSVO in individuals 18 through 59 years of age considered to be at increased risk of LRTD caused by RSV due to certain chronic medical conditions [see Clinical Studies (14.3)]. This study was conducted in the US. Demographic characteristics among individuals who received ABRYSVO and those who received placebo were generally similar with regard to age, race, and ethnicity; 43% and 32% of participants in the ABRYSVO and placebo groups, respectively, were male. Of the participants in the study, 68% were White, 24% were Black or African American, 5% were Asian, and 22% were Hispanic/Latino. Fifty-two percent (52%) were 18 to 49 years and 48% were 50 to 59 years. The median age of participants was 49 years. The vaccine and placebo groups were similar with regard to the prevalence of underlying medical conditions: one or more chronic pulmonary condition (52%), diabetes (43%), one or more other disease (liver, renal, neurologic, hematologic, or other metabolic disease) (31%), and one or more cardiovascular condition (8%).

Solicited local and systemic adverse reactions that occurred within 7 days following study vaccination were self‑reported in electronic diaries or were reported to an investigator. Unsolicited adverse events were collected for 1 month after study vaccination; serious adverse events (SAEs) were collected for 6 months after study vaccination.

Solicited Local and Systemic Reactions in Study 4

Solicited local and systemic reactions reported within 7 days after vaccination in Study 4 are presented in Tables 6 and 7.

Table 6 Percentage of Participants 18 through 59 Years of Age at Increased Risk of LRTD caused by RSV with Local Reactions Reported, by Maximum Severity, within 7 Days after Vaccination – Study 4 [NCT05842967]
Local Reactions | ABRYSVO; N=451 [N = number of participants reporting at least one response in the e-diary.]; % | PLACEBO; N=225; %
Injection site pain [Mild: does not interfere with activity; moderate: some interference with activity; severe: prevents daily activity.]
Any [Any includes all participants who reported a reaction as mild, moderate, or severe during Day 1 to Day 7 after vaccination.] | 35.3 | 10.7
Mild | 29.7 | 10.2
Moderate | 5.5 | 0.4
Severe | 0 | 0
Redness [Mild: >2 cm to 5 cm; moderate: >5 cm to 10 cm; severe: >10 cm (for data reported from e-diaries).]
Any | 6.0 | 0.4
Mild | 3.8 | 0
Moderate | 2.2 | 0.4
Severe | 0 | 0
Swelling
Any | 7.1 | 0.9
Mild | 4.0 | 0.4
Moderate | 2.9 | 0.4
Severe | 0.2 | 0

Table 7 Percentage of Participants 18 through 59 Years of Age at Increased Risk of LRTD caused by RSV with Systemic Reactions Reported, by Maximum Severity, within 7 Days after Vaccination – Study 4 [NCT05842967]
Systemic Reactions | ABRYSVO; N=451 [N = number of participants reporting at least one response in the e-diary.]; % | PLACEBO; N=225; %
Fever (≥38.0℃)
≥38.0°C | 1.6 | 1.3
≥38.0°C to 38.4°C | 0.4 | 0.4
>38.4°C to 38.9°C | 1.1 | 0.9
>38.9°C to 40.0°C | 0 | 0
Fatigue [Mild: does not interfere with activity; moderate: some interference with activity; severe: prevents daily routine activity.]
Any [Any includes all participants who reported a reaction as mild, moderate, or severe during Day 1 to Day 7 after vaccination.] | 37.3 | 38.2
Mild | 18.2 | 22.2
Moderate | 18.2 | 15.6
Severe | 0.9 | 0.4
Headache
Any | 28.4 | 30.2
Mild | 20.8 | 18.7
Moderate | 7.3 | 11.6
Severe | 0.2 | 0
Muscle pain
Any | 24.4 | 16.0
Mild | 15.7 | 9.8
Moderate | 8.6 | 6.2
Severe | 0 | 0
Joint pain
Any | 12.4 | 10.2
Mild | 7.1 | 4.0
Moderate | 5.1 | 6.2
Severe | 0.2 | 0
Nausea
Any | 11.8 | 10.2
Mild | 9.3 | 8.9
Moderate | 2.4 | 0.9
Severe | 0 | 0.4
Vomiting [Mild: 1 to 2 times in 24 hours; moderate: >2 times in 24 hours; severe: requires intravenous hydration.]
Any | 2.0 | 1.3
Mild | 1.6 | 0.4
Moderate | 0.4 | 0.9
Severe | 0 | 0
Diarrhea [Mild: 2 to 3 loose stools in 24 hours; moderate: 4 to 5 loose stools in 24 hours; severe: 6 or more loose stools in 24 hours.]
Any | 14.9 | 16.9
Mild | 11.1 | 12.4
Moderate | 3.1 | 3.6
Severe | 0.7 | 0.9

Solicited local and systemic reactions had a median duration of 1-2 days.

Unsolicited Adverse Events in Study 4

Unsolicited adverse events occurring within 1 month after vaccination were reported in 7.1% and 7.6% of participants who received ABRYSVO and placebo, respectively. One case of urticaria occurred on the same day as vaccine administration and was considered related to ABRYSVO.

Serious Adverse Events in Study 4

In Study 4, SAEs were reported by 1.1% of participants in the ABRYSVO group and 3.1% in the placebo group. No SAEs were assessed as related to study vaccination.

Serious Adverse Events Reported from Other Studies

Anaphylaxis was reported in a participant enrolled in a study (NCT06473519) in the US, with onset of symptoms 10 minutes after vaccination with ABRYSVO. The study enrolled healthy female participants 18 years through 49 years of age (n=450).

Concomitant Administration of ABRYSVO with a Seasonal Inactivated Influenza Vaccine

Study 5 (NCT05301322) was a Phase 3, multicenter, parallel group, placebo-controlled, randomized, double-blind study conducted in Australia in adults ≥65 years of age. The study enrolled healthy adults and adults with stable chronic medical conditions not requiring significant change in therapy or hospitalization for worsening disease 6 weeks before enrollment. Participants were enrolled into one of two groups. Participants in the concomitant administration group (n=703) received ABRYSVO and Influenza Vaccine, Adjuvanted (FLUAD® QUADRIVALENT) concomitantly and placebo one month later. Participants in the sequential administration group (n=691) received FLUAD QUADRIVALENT and placebo concomitantly and ABRYSVO one month later.

Within 7 days following vaccine administration, fatigue was reported by 30.0% of participants who received ABRYSVO administered concomitantly with FLUAD QUADRIVALENT, 19.1% who received ABRYSVO administered alone, and 27.1% who received FLUAD QUADRIVALENT and placebo concomitantly. There were no other notable differences in reported solicited local and systemic adverse reactions within 7 days following ABRYSVO administered concomitantly with FLUAD QUADRIVALENT compared to ABRYSVO administered alone. Participants were followed for SAEs from administration of the first dose of vaccine through 1 month following the last vaccination. No SAEs were considered related to vaccination.

6.2 Postmarketing Experience

The following adverse reactions have been identified from spontaneous reports during postmarketing use of ABRYSVO. Because these reactions are reported voluntarily from a population of uncertain size, it is not always possible to reliably estimate their frequency or establish a causal relationship to the vaccine.

Immune System Disorders: Anaphylaxis and other hypersensitivity reactions including rash and urticaria.

Nervous System Disorders: Guillain‑Barré syndrome.

Postmarketing Observational Study of the Risk of Guillain‑Barré Syndrome following Vaccination with ABRYSVO

The association between vaccination with ABRYSVO and Guillain‑Barré syndrome (GBS) was evaluated among Medicare beneficiaries 65 years of age and older. Using Medicare claims data, between May 2023 through July 2024, vaccinations with ABRYSVO were identified through Current Procedural Terminology (CPT)/Healthcare Common Procedure Coding System (HCPCS) codes and National Drug Codes, and potential cases of hospitalized GBS among recipients of ABRYSVO were identified through International Classification of Diseases (ICD) codes. GBS diagnoses in claims data were confirmed by medical record review when available.

The risk of GBS following vaccination with ABRYSVO was assessed in self-controlled case series analyses using a risk window of 1 to 42 days post-vaccination and a control window of 43 to 90 days post-vaccination. The analyses of all GBS cases based on claims data suggest an increased risk of GBS during the 42 days following vaccination with ABRYSVO, with an incidence rate ratio (GBS cases in the risk window/control window) of 2.02 (95% CI: 0.93, 4.40) and an estimated 9 excess cases of GBS per million doses administered to individuals 65 years of age and older. The background risk of GBS in a study population influences the excess GBS case estimate and may differ between studies, precluding direct comparison to excess GBS case estimates from other vaccine studies or populations.

The analyses of GBS diagnoses in claims data were supported by analyses of GBS cases confirmed by medical record review and by analyses of GBS cases in individuals who received ABRYSVO alone, without other concomitantly administered vaccines. While the results of this observational study suggest an increased risk of GBS with ABRYSVO, available evidence is insufficient to establish a causal relationship.

7 DRUG INTERACTIONS

In Study 6 (NCT04071158) in a concomitant administration study of ABRYSVO and a Tetanus Toxoid, Reduced Diphtheria Toxoid and Acellular Pertussis Vaccine, Adsorbed (Tdap) in non-pregnant women, no safety concerns were identified. Immune responses to RSV A, RSV B, diphtheria, and tetanus were non-inferior to those after separate administration. Lower geometric mean antibody concentrations (GMCs) to the acellular pertussis antigens (pertussis toxin [PT], filamentous hemagglutinin (FHA), and pertactin [PRN]) were measured when ABRYSVO was administered concomitantly with Tdap compared to pertussis GMCs when Tdap was administered alone [see Clinical Studies (14.5)].

Concomitant administration of Tdap with ABRYSVO in pregnant individuals has not been studied.

8 USE IN SPECIFIC POPULATIONS

8.1 Pregnancy

Pregnancy Exposure Registry

There is a pregnancy exposure registry that monitors pregnancy outcomes in individuals exposed to ABRYSVO during pregnancy. Individuals who received ABRYSVO during pregnancy are encouraged to contact, or have their healthcare provider contact, 1-800-616-3791 to enroll in or obtain information about the registry.

Risk Summary

All pregnancies have a risk of birth defect, loss, or other adverse outcomes. In the US general population, the estimated background risk of major birth defects and miscarriages in clinically recognized pregnancies is 2% to 4%, and 15% to 20%, respectively, and the estimated background risk of fetal deaths after 20 weeks is 0.6%.

Study 1 enrolled 7,386 pregnant individuals who were randomized 1:1 and received ABRYSVO or placebo (0.5 mL dose, containing the same buffer ingredients in the same quantities as in a single dose of ABRYSVO [see Description (11)]) revealed no evidence for vaccine-associated increase in the risk of congenital anomalies or fetal deaths. Study 2 evaluated 115 pregnant individuals who received ABRYSVO and 117 who received placebo. A numerical imbalance in preterm births in ABRYSVO recipients was observed compared to placebo recipients in these two clinical studies. Available data are insufficient to establish or exclude a causal relationship between preterm birth and ABRYSVO [see Warnings and Precautions (5.2), Adverse Reactions (6.1), Clinical Considerations (8.1), Data (8.1) and Clinical Studies (14.1)].

A developmental toxicity study was performed in female rabbits administered a vaccine formulation containing two times the antigen content of a single human dose of ABRYSVO prior to and during gestation. The study showed no evidence of harm to the fetus or to postnatal survival, growth, or development (see Animal Data).

Clinical Considerations

Maternal Adverse Reactions

In Study 1, 3,698 pregnant individuals received ABRYSVO and 3,687 received placebo. Local and systemic adverse reactions occurred with greater frequency in the ABRYSVO group. Serious adverse reactions observed in pregnant individuals at a higher rate in the ABRYSVO group compared to the placebo group included pre-eclampsia (1.8% versus 1.4%) and gestational hypertension (1.2% versus 1.1%) [see Adverse Reactions (6.1)].

ABRYSVO has not been studied in pregnant individuals less than 24 weeks gestational age, and those at increased risk for preterm birth.

Fetal/Neonatal Adverse Reactions

The infant safety population included 3,659 and 3,646 infants born to individuals in the ABRYSVO or placebo group, respectively. There were 10 (0.3%) fetal deaths in the ABRYSVO group and 9 (0.2%) in the placebo group. Among the infants born to individuals in the ABRYSVO group and in the placebo group, 207 (5.7%) and 172 (4.7%), respectively, were born preterm [see Warnings and Precautions (5.2), Adverse Reactions (6.1) and Clinical Studies (14.1)]. Low birth weight was observed in 5.1% of participants in the ABRYSVO group versus 4.3% in the placebo group, and neonatal jaundice was observed in 7.3% in the ABRYSVO group versus 6.9% in the placebo group. [see Adverse Reactions (6.1)]. For mortality in the neonatal period among infants born to pregnant individuals in Study 1, there were 3 deaths in the ABRYSVO group and 5 in the placebo group, and for overall mortality including after the neonatal period there were 8 deaths in the ABRYSVO group and 14 in the placebo group. Congenital abnormalities were reported in 5.6% in the ABRYSVO group and 6.7% in the placebo group.

Available data are insufficient to establish or exclude a causal relationship between preterm birth and ABRYSVO. To avoid the potential risk of preterm birth with use of ABRYSVO before 32 weeks of gestation, administer ABRYSVO as indicated in pregnant individuals at 32 through 36 weeks gestational age.

Data

Human Data

In Study 1, 3,698 pregnant individuals received ABRYSVO and 3,687 received placebo at 24 through 36 weeks’ gestation. The infant safety population included 3,659 and 3,646 infants born to individuals in the ABRYSVO or placebo group, respectively. Among the infants born to individuals in the ABRYSVO group and in the placebo group, 207 (5.7%) and 172 (4.7%), respectively, had adverse events of preterm birth and 205 (5.6%) and 245 (6.7%), respectively, had reported congenital malformations or anomalies. There were 10 (0.3%) fetal deaths in the ABRYSVO group and 9 (0.2%) in the placebo group.

Animal Data

A pre- and post-natal developmental toxicity study with an embryo-fetal developmental toxicity phase was performed in female New Zealand White rabbits. Rabbits were administered 4 doses by intramuscular injection: at 3 weeks and at 1 week prior to mating, and on gestation days 10 and 24. On each occasion, rabbits received 0.5 mL of a vaccine formulation containing twice the antigen content of F glycoproteins of RSV A and RSV B (120 mcg RSV preF A and 120 mcg RSV preF B), stabilized in prefusion conformation as contained in a single human dose of ABRYSVO [see Description (11)]. No adverse effects on mating, female fertility, or on embryo/fetal or post-natal survival, growth, or development were observed. There were no vaccine-related fetal malformations or variations.

8.2 Lactation

Risk Summary

It is not known whether ABRYSVO is excreted in human milk. Data are not available to assess the effects of ABRYSVO on the breastfed infant or on milk production/excretion. The developmental and health benefits of breastfeeding should be considered along with the mother’s clinical need for ABRYSVO and any potential adverse effects on the breastfed child from ABRYSVO or from the underlying maternal condition. For preventative vaccines, the underlying maternal condition is susceptibility to disease prevented by the vaccine.

8.4 Pediatric Use

The safety and effectiveness of ABRYSVO to prevent RSV LRTD and severe RSV LRTD in infants born to individuals vaccinated at younger than 10 years of age have not been established.

The safety and effectiveness of ABRYSVO to prevent RSV LRTD in non-pregnant individuals younger than 18 years of age via active immunization have not been established.

8.5 Geriatric Use

ABRYSVO is approved for use in individuals 60 years of age and older. In Study 3 and Study 7, of the 18,681 recipients who received ABRYSVO 63% (n=11,695) were aged 60-69 years of age, 32% (n=5,958) were 70-79 years of age and 5% (n=1,027) were ≥80 years of age [see Adverse Reactions (6.1), Use in Specific Populations (8.6), and Clinical Studies (14.2)].

8.6 Immunocompromised Individuals 18 Years of Age and Older

Study 7 Substudy B (NCT05842967) was a Phase 3 single‑arm, open‑label, multicenter study to assess the safety and immunogenicity of ABRYSVO in immunocompromised individuals ≥18 years of age. A total of 203 participants received one dose of ABRYSVO and 201 participants received a second dose of ABRYSVO one month later (an unapproved dosing regimen).

In Study 7, 46% of participants were male, 74% were White, 20% were Black or African American, 4% were Asian, and 5% were Hispanic/Latino. Forty‑seven percent (47%) were 18 through 59 years of age and 53% were ≥60 years of age. The median age of participants was 60 years. In this study, 48% had an autoimmune inflammatory disorder on active immunomodulator therapy, 37% had a history of solid organ transplant on maintenance immunosuppressive therapy, 15% had end‑stage renal disease on hemodialysis, and 3% were on therapy for advanced non‑small cell lung cancer.

Solicited local and systemic reactions that occurred within 7 days following study vaccination were collected. Unsolicited adverse events were collected for 1 month after dose 2 of study vaccination, and serious adverse events were collected for 6 months following dose 2 of study vaccination.

The reactogenicity profile in immunocompromised participants was similar to those observed in other studies [see Adverse Reactions (6.1)], with the following exceptions: Following vaccination with ABRYSVO, pain at the injection site (in up to 46.8% of participants) was the most frequently reported solicited local reaction. The percentages of participants 18 through 59 years of age and ≥60 years of age reporting any solicited local reaction were higher after dose 2 (46.8% and 34.3%, respectively) than dose 1 (26.0% and 19.6%, respectively). There were no severe solicited local reactions. In this study, at least one severe solicited systemic reaction, defined as those preventing daily routine activity (predominantly fatigue as well as headache, muscle pain, and joint pain), was reported in 2.1% and 4.7% of participants 18 through 59 years and ≥60 years of age, respectively, after dose 1 and reported in <1% of participants after dose 2.

One 66 year old participant reported atrial fibrillation and atrial flutter with onset of symptoms 15 days after dose 1. The currently available information on atrial fibrillation and atrial flutter is insufficient to determine a causal relationship to the vaccine [see Adverse Reactions (6.1)].

After a single dose of ABRYSVO, the seroresponse rates [defined as achieving a ≥4‑fold rise in neutralizing titers for RSV A and RSV B from baseline if the baseline measurement is above the lower limit of quantitation (LLOQ) or a post‑vaccination assay result ≥4 × LLOQ if the baseline measurement is below the LLOQ] in the overall study population were 70.2% (95% CI 63.1%, 76.6%) and 71.3% (95% CI 64.2%, 77.6%) for RSV A and RSV B, respectively, 1 month after vaccination. Seroresponse rates in the overall study population did not further increase with a second dose of ABRYSVO 1 month after the first dose [70.2% (95% CI 63.1%, 76.6%) and 71.3% (95% CI 64.2%, 77.6%) for RSV A and RSV B, respectively]. In the subgroup with a history of solid organ transplant, seroresponse rates were 58.2% (95% CI 45.5%, 70.2%) 1 month after the first dose for both RSV A and RSV B, and 65.7% (95% CI 53.1%, 76.8%) and 64.2% (95% CI 51.5%, 75.5%) 1 month after the second dose for RSV A and RSV B, respectively. The data from this study do not establish the effectiveness of ABRYSVO in immunocompromised individuals.

11 DESCRIPTION

ABRYSVO (Respiratory Syncytial Virus Vaccine) is a sterile solution for intramuscular use. The vaccine is supplied as a vial of Lyophilized Antigen Component that is reconstituted at the time of use with a Sterile Water Diluent Component. The antigen component contains recombinant RSV preF A and RSV preF B.

The RSV preF A and RSV preF B recombinant proteins are expressed in genetically engineered Chinese Hamster Ovary cell lines grown in suspension culture using chemically-defined media, without antibiotics or animal-derived components. The recombinant proteins are purified through a series of column chromatography and filtration steps followed by formulation, filling into vials, and lyophilization.

After reconstitution, a single dose of ABRYSVO is formulated to contain 120 mcg of RSV stabilized prefusion F proteins (60 mcg RSV preF A and 60 mcg RSV preF B) per 0.5 mL. ABRYSVO also contains the following buffer ingredients: 0.11 mg tromethamine, 1.04 mg tromethamine hydrochloride, 11.3 mg sucrose, 22.5 mg mannitol, 0.08 mg polysorbate 80, and 1.1 mg sodium chloride per 0.5 mL. ABRYSVO is a sterile, clear, and colorless solution.

ABRYSVO contains no preservatives. Each dose may also contain residual amounts of host cell proteins (≤0.1% w/w) and DNA (<0.4 ng/mg of total protein) from the manufacturing process.

The Act-O-Vial stoppers, vial stoppers and tip cap and rubber plunger of the prefilled syringe are not made with natural rubber latex.

12 CLINICAL PHARMACOLOGY

12.1 Mechanism of Action

Active Immunization

ABRYSVO induces an immune response against RSVpreF that protects against lower respiratory tract disease caused by RSV.

Passive Immunization

Antibodies to RSV antigens from individuals vaccinated in pregnancy are transferred transplacentally to protect infants younger than 6 months of age against LRTD and severe LRTD caused by RSV.

13 NONCLINICAL TOXICOLOGY

13.1 Carcinogenesis, Mutagenesis, Impairment of Fertility

ABRYSVO has not been evaluated for the potential to cause carcinogenicity, genotoxicity, or impairment of male fertility. A developmental toxicity study in female rabbits revealed no evidence of impaired female fertility after administration of a vaccine formulation containing two times the antigen content of a single human dose of ABRYSVO [see Use in Specific Populations (8.1)].

14 CLINICAL STUDIES

14.1 Study in Pregnant Individuals for Efficacy in Their Infants from Birth Through 6 Months of Age

Study 1 (NCT04424316) was a Phase 3 study that assessed the efficacy of ABRYSVO in the prevention of RSV-associated lower respiratory tract disease (LRTD) in infants born to individuals vaccinated during pregnancy. The study evaluated the efficacy of ABRYSVO to prevent RSV-associated LRTD and severe RSV-LRTD in infants within 90, 120, 150, and 180 days after birth. Participants were randomized (1:1) to receive ABRYSVO (0.5 mL dose) or placebo (0.5 mL dose containing the same buffer ingredients in the same quantities as in a single dose of ABRYSVO [see Description (11)]). This study included sites in both the northern and southern hemispheres. Vaccine efficacy (VE) was defined as the relative risk reduction of the endpoints of severe LRTD caused by RSV and LRTD cause by RSV in infants born to individuals who received ABRYSVO compared to infants born to individuals who received placebo. The demographic characteristics of Study 1 are described in Clinical Trials Experience Section 6.1.

Maternal participants were randomized (1:1) to receive ABRYSVO (3,711) or placebo (3,709). RSV-associated LRTD in infants was defined as a medically attended visit with a reverse transcription-polymerase chain reaction (RT-PCR) confirmed RSV illness with one or more of the following respiratory symptoms: tachypnea (respiratory rate ≥60 breaths/minute [<2 months of age], ≥50 breaths/minute [≥2 to 12 months of age], or ≥40 breaths/minute [≥12-24 months of age]); SpO2 measured in room air <95%; chest wall indrawing. RSV-associated severe LRTD was a subset defined as meeting the LRTD RSV criteria plus at least one of the following: tachypnea (respiratory rate ≥70 breaths per minute [<2 months of age], ≥60 breaths per minute [≥2 to 12 months of age], or ≥50 bpm [≥12 to 24 months of age]); SpO2 measured in room air <93%; high-flow nasal cannula or mechanical ventilation (invasive or noninvasive), ICU admission for >4 hours and/or failure to respond/unconscious. Secondary efficacy endpoints included hospitalizations due to RSV.

The VE results met the statistical criterion for success (a CI lower bound >20%) for reducing severe LRTD due to RSV, at all timepoints to within 180 days. The VE results did not meet the statistical criterion for success (a CI lower bound >20%) for reducing LRTD due to RSV; however, clinically meaningful efficacy was observed after 90 days through 180 days after birth.

Vaccine efficacy information is presented in Tables 8 to 12.

Table 8 Vaccine Efficacy of ABRYSVO Against Severe LRTD Caused by RSV – Infants From Birth Through 6 Months of Age by Active Immunization of Pregnant Individuals (Study 1) [The prespecified success criterion was met for this endpoint evaluation]
Time Period | ABRYSVO; Number of Cases; N=3,495 [Evaluable efficacy population] | PLACEBO; Number of Cases; N=3,480 | VE (%); (CI) [99.5% CI at 90 days; 97.58% CI at later intervals]
90 days | 6 | 33 | 81.8 (40.6, 96.3)
120 days | 12 | 46 | 73.9 (45.6, 88.8)
150 days | 16 | 55 | 70.9 (44.5, 85.9)
180 days | 19 | 62 | 69.4 (44.3, 84.1)
CI – confidence interval; N – number of participants; RSV – respiratory syncytial virus; VE – vaccine efficacy

Table 9 Vaccine Efficacy of ABRYSVO Against LRTD Caused by RSV – Infants From Birth Through 6 Months of Age by Active Immunization of Pregnant Individuals (Study 1) [The prespecified success criterion (a CI lower bound >20%) was not met for this endpoint evaluation at 90 days]
Time Period | ABRYSVO; Number of Cases; N=3,495 [Evaluable efficacy population] | PLACEBO; Number of Cases; N=3,480 | VE (%); (CI) [99.5% CI at 90 days; 97.58% CI at later intervals]
90 days | 24 | 56 | 57.1 (14.7, 79.8)
120 days | 35 | 81 | 56.8 (31.2, 73.5)
150 days | 47 | 99 | 52.5 (28.7, 68.9)
180 days | 57 | 117 | 51.3 (29.4, 66.8)
CI – confidence interval; N – number of participants; RSV – respiratory syncytial virus; VE – vaccine efficacy

Table 10 Vaccine Efficacy of ABRYSVO Against Severe LRTD Caused by RSV – Infants From Birth Through 6 Months of Age by Active Immunization of Pregnant Individuals at 32 Through 36 Weeks Gestational Age (Study 1) [This descriptive subgroup analysis was not controlled for multiple comparisons; results from 90 days and 180 days are presented.]
Time Period | ABRYSVO; Number of Cases; N=1,572 [Evaluable efficacy population] | PLACEBO; Number of Cases; N=1,539 | VE (%); (CI) [95% CI]
90 days | 1 | 11 | 91.1 (38.8, 99.8)
180 days | 6 | 25 | 76.5 (41.3, 92.1)
CI – confidence interval; N – number of participants; n – number of cases; RSV – respiratory syncytial virus; VE – vaccine efficacy

Table 11 Vaccine Efficacy of ABRYSVO Against LRTD Caused by RSV – Infants From Birth Through 6 Months of Age by Active Immunization of Pregnant Individuals at 32 Through 36 Weeks Gestational Age (Study 1) [This descriptive subgroup analysis was not controlled for multiple comparisons; results from 90 days and 180 days are presented.]
Time Period | ABRYSVO; Number of Cases; N=1,572 [Evaluable efficacy population] | PLACEBO; Number of Cases; N=1,539 | VE (%); (CI) [95% CI]
90 days | 14 | 21 | 34.7 (-34.6, 69.3)
180 days | 24 | 55 | 57.3 (29.8, 74.7)
CI – confidence interval; N – number of participants; n – number of cases; RSV – respiratory syncytial virus; VE – vaccine efficacy

Table 12 Vaccine Efficacy of ABRYSVO Against Hospitalization Due to RSV – Infants From Birth Through 6 Months of Age by Active Immunization of Pregnant Individuals (Study 1) [NCT04424316]
Time Period | ABRYSVO; Number of Cases; N=3,495 [Evaluable efficacy population] | PLACEBO; Number of Cases; N=3,480 | VE (%); (CI) [99.17% CI]
90 days | 10 | 31 | 67.7 (15.9, 89.5)
120 days | 15 | 37 | 59.5 (8.3, 83.7)
150 days | 17 | 39 | 56.4 (5.2, 81.5)
180 days | 19 | 44 | 56.8 (10.1, 80.7)
CI – confidence interval; N – number of participants; n – number of cases; RSV – respiratory syncytial virus; VE – vaccine efficacy

14.2 Efficacy in Individuals 60 Years of Age and Older

Study 3 (NCT05035212) was a Phase 3, multicenter, randomized, double-blind, placebo-controlled study to assess the efficacy and safety of ABRYSVO in the prevention of RSV-associated lower respiratory tract disease in individuals 60 years of age and older. Participants were followed for up to two RSV seasons, approximately 25 months.

Participants were randomized (1:1) to receive ABRYSVO (n=18,487) or placebo (n=18,479). Randomization was stratified by age, 60-69 years (n=23,151, 63%), 70-79 years (n=11,782, 32%), and ≥80 years (n=2,031, 6%). Healthy adults and adults with stable chronic diseases were included. Among enrolled participants 16% had stable chronic cardiopulmonary conditions such as chronic obstructive pulmonary disease (COPD), asthma, or congestive heart failure (CHF).

Starting 14 days after study vaccination (study Day 15), all participants were actively monitored for onset of acute respiratory illness (ARI) symptoms: new or increased sore throat, nasal congestion, nasal discharge, cough, wheezing, sputum production, or shortness of breath. If the participant experienced 1 or more ARI symptoms, a mid-turbinate nasal swab was collected within 7 days of onset of symptoms and tested by reverse transcriptase polymerase chain reaction (RT-PCR) for RSV.

RSV-associated lower respiratory tract disease (RSV-LRTD) was evaluated in Study 3. A case of RSV-LRTD was defined as an RT-PCR confirmed RSV illness with two or more, or three or more, of the following respiratory symptoms within 7 days of symptom onset and lasting more than 1 day during the same illness: new or increased cough, wheezing, sputum production, shortness of breath, or tachypnea (≥25 breaths/min or 15% increase from resting baseline). A case of RSV-associated severe lower respiratory tract disease was defined as a case meeting the RSV-LRTD criteria plus at least one of the following: hospitalization due to RSV-LRTD, new or increased oxygen supplementation, or mechanical ventilation including Continuous Positive Airway Pressure (CPAP).

Vaccine efficacy (VE) against RSV-LRTD, defined as the relative risk reduction of first episode of RSV-LRTD in the ABRYSVO group compared to the placebo group in the first RSV season, was assessed.

The primary analysis of efficacy was conducted when 44 first-episode RSV-LRTD cases with ≥2 symptoms had accrued in the first RSV season. The study met the pre-specified success criteria for demonstration of efficacy of ABRYSVO for the primary objectives of prevention of RSV-LRTD with ≥2 symptoms and prevention of RSV-LRTD with ≥3 symptoms.

Vaccine efficacy information for the primary analysis is presented in Table 13.

Table 13 Vaccine Efficacy of ABRYSVO Against RSV-LRTD - Individuals 60 Years of Age and Older – Primary Analysis (Study 3) [NCT05035212]
Efficacy Endpoint; 7 months median follow-up | ABRYSVO; N=16,306 [Evaluable efficacy population]; n | Placebo; N=16,308; n | VE (%); (96.66% CI)
First episode of RSV-associated lower respiratory tract disease with ≥2 symptoms [RSV-associated LRTD symptoms included the following: new or increased cough, wheezing, sputum production, shortness of breath, or tachypnea (≥25 breaths/min or 15% increase from resting baseline).] | 11 | 33 | 66.7 (28.8, 85.8)
First episode of RSV-associated lower respiratory tract disease with ≥3 symptoms | 2 | 14 | 85.7 (32.0, 98.7)
CI – confidence interval; N – number of participants; n = number of cases; RSV – respiratory syncytial virus; VE – vaccine efficacy (VE based on case count ratio is calculated as 1-(P/[1-P]), where P is the number of cases in the ABRYSVO group divided by the total number of cases combined ABRYSVO and placebo)

There were 2 cases of RSV-associated severe lower respiratory tract disease in the placebo group and no cases in the ABRYSVO group during the first RSV season. In the second RSV season, 1 case was reported in each group.

Descriptive vaccine efficacy analyses at the end of the first RSV season and combined across the two RSV seasons are presented in Tables 14 and 15.

Table 14 Descriptive Vaccine Efficacy of ABRYSVO Against RSV LRTD - Individuals 60 Years of Age and Older, End of First RSV Season (Study 3) [NCT05035212]
Efficacy Endpoint | Analysis Population | ABRYSVO; n/N | Placebo; n/N | VE (%); (95% CI)
7.4 months median follow-up
First episode of RSV-associated lower respiratory tract disease with ≥2 symptoms [RSV-associated LRTD symptoms included the following: new or increased cough, wheezing, sputum production, shortness of breath, or tachypnea (≥25 breaths/min or 15% increase from resting baseline).] | Overall [Evaluable efficacy population.] | 15/18,050 | 43/18,074 | 65.1 (35.9, 82.0)
First episode of RSV-associated lower respiratory tract disease with ≥2 symptoms [RSV-associated LRTD symptoms included the following: new or increased cough, wheezing, sputum production, shortness of breath, or tachypnea (≥25 breaths/min or 15% increase from resting baseline).] | Age 60-69 years | 10/11,305 | 25/11,351 | 60.0 (13.8, 82.9)
First episode of RSV-associated lower respiratory tract disease with ≥2 symptoms [RSV-associated LRTD symptoms included the following: new or increased cough, wheezing, sputum production, shortness of breath, or tachypnea (≥25 breaths/min or 15% increase from resting baseline).] | Age 70-79 years | 4/5,750 | 12/5,742 | 66.7 (-10.0, 92.2) [VE cannot be reliably estimated due to the small number of accrued cases in the subgroup.]
First episode of RSV-associated lower respiratory tract disease with ≥2 symptoms [RSV-associated LRTD symptoms included the following: new or increased cough, wheezing, sputum production, shortness of breath, or tachypnea (≥25 breaths/min or 15% increase from resting baseline).] | Age ≥ 80 years | 1/995 | 6/981 | 83.3 (-37.4, 99.6)
First episode of RSV-associated lower respiratory tract disease with ≥2 symptoms [RSV-associated LRTD symptoms included the following: new or increased cough, wheezing, sputum production, shortness of breath, or tachypnea (≥25 breaths/min or 15% increase from resting baseline).] | With ≥1 significant underlying condition [Subgroup of evaluable efficacy population with ≥1 significant underlying condition i.e. heart disease (including congestive heart failure), lung disease (including chronic obstructive pulmonary disease), asthma, diabetes mellitus, liver disease, renal disease, and current tobacco use.] | 8/9,387 | 22/9,448 | 63.6 (15.2, 86.0)
First episode of RSVassociated lower respiratory tract disease with ≥3 symptoms | Overall [Subgroup analyses by age are not presented for RSV-LRTD with ≥3 symptoms due to the limited number of accrued cases in the age subgroups during the first RSV season.] | 2/18,050 | 18/18,074 | 88.9 (53.6, 98.7)
First episode of RSVassociated lower respiratory tract disease with ≥3 symptoms | With ≥1 significant underlying condition | 2/9,387 | 11/9,448 | 81.8 (16.7, 98.0)
CI – confidence interval; N – number of participants; n = number of cases; RSV – respiratory syncytial virus; VE – vaccine efficacy (VE based on case count ratio is calculated as 1-(P/[1-P]), where P is the number of cases in the ABRYSVO group divided by the total number of cases)

For RSV-A associated LRTD at the end of the first season, descriptive VE was 81.3% (95% CI 34.5, 96.5) for cases with ≥2 LRTD symptoms and 80.0% (95% CI -78.7, 99.6) for cases with ≥3 LRTD symptoms. For RSV-B associated LRTD at the end of the first season, descriptive VE was 53.8% (95% CI 5.2, 78.8) for cases with ≥2 LRTD symptoms and 91.7% (95% CI 43.7, 99.8) for cases with ≥3 LRTD symptoms.

In the second RSV season, VE against RSV-associated LRTD with ≥2 symptoms was 55.7% (95% CI 34.7, 70.4; 39 cases in the ABRYSVO group and 88 cases in the placebo group) and with ≥3 symptoms was 77.8% (95% CI 51.4, 91.1; 8 cases in the ABRYSVO group and 36 cases in the placebo group). The median duration of follow-up was 7.7 months in the second season.

Table 15 Descriptive Vaccine Efficacy of ABRYSVO Against RSV LRTD - Individuals 60 Years of Age and Older, Across Two RSV Seasons (Study 3) [NCT05035212]
Efficacy Endpoint | Analysis Population | ABRYSVO; n/N | Placebo; n/N | VE (%); (95% CI)
16.9 months median time since vaccination
First episode of RSV-associated lower respiratory tract disease with ≥2 symptoms [RSV-associated LRTD symptoms included the following: new or increased cough, wheezing, sputum production, shortness of breath, or tachypnea (≥25 breaths/min or 15% increase from resting baseline).] | Overall [Evaluable efficacy population.] | 54/18,050 | 131/18,074 | 58.8 (43.0, 70.6)
First episode of RSV-associated lower respiratory tract disease with ≥2 symptoms [RSV-associated LRTD symptoms included the following: new or increased cough, wheezing, sputum production, shortness of breath, or tachypnea (≥25 breaths/min or 15% increase from resting baseline).] | Age 60-69 years | 34/11,305 | 80/11,351 | 57.5 (35.8, 72.4)
First episode of RSV-associated lower respiratory tract disease with ≥2 symptoms [RSV-associated LRTD symptoms included the following: new or increased cough, wheezing, sputum production, shortness of breath, or tachypnea (≥25 breaths/min or 15% increase from resting baseline).] | Age 70-79 years | 15/5,750 | 40/5,742 | 62.5 (30.6, 80.8)
First episode of RSV-associated lower respiratory tract disease with ≥2 symptoms [RSV-associated LRTD symptoms included the following: new or increased cough, wheezing, sputum production, shortness of breath, or tachypnea (≥25 breaths/min or 15% increase from resting baseline).] | Age ≥ 80 years | 5/995 | 11/981 | 54.5 (-41.9, 87.6) [VE cannot be reliably estimated due to the small number of accrued cases in the subgroup.]
First episode of RSV-associated lower respiratory tract disease with ≥2 symptoms [RSV-associated LRTD symptoms included the following: new or increased cough, wheezing, sputum production, shortness of breath, or tachypnea (≥25 breaths/min or 15% increase from resting baseline).] | With ≥1 significant underlying condition [Subgroup of evaluable efficacy population with ≥1 significant underlying condition i.e. heart disease (including congestive heart failure), lung disease (including chronic obstructive pulmonary disease), asthma, diabetes mellitus, liver disease, renal disease, and current tobacco use.] | 36/9,387 | 71/9,448 | 49.3 (23.2, 67.0)
First episode of RSV-associated lower respiratory tract disease with ≥3 symptoms | Overall | 10/18,050 | 54/18,074 | 81.5 (63.3, 91.6)
First episode of RSV-associated lower respiratory tract disease with ≥3 symptoms | Age 60-69 years | 7/11,305 | 38/11,351 | 81.6 (58.2, 93.1)
First episode of RSV-associated lower respiratory tract disease with ≥3 symptoms | Age 70-79 years | 3/5,750 | 11/5,742 | 72.7 (-3.2, 95.1)
First episode of RSV-associated lower respiratory tract disease with ≥3 symptoms | Age ≥ 80 years | 0/995 | 5/981 | 100.0 (-9.1, 100.0)
First episode of RSV-associated lower respiratory tract disease with ≥3 symptoms | With ≥1 significant underlying condition | 9/9,387 | 34/9,448 | 73.5 (43.6, 88.8)
CI – confidence interval; N – number of participants; n = number of cases; RSV – respiratory syncytial virus; VE – vaccine efficacy (VE based on case count ratio is calculated as 1-(P/[1-P]), where P is the number of cases in the ABRYSVO group divided by the total number of cases)

For RSV-A associated LRTD across two RSV seasons, descriptive VE was 66.3% (95% CI 47.2, 79.0) for cases with ≥2 LRTD symptoms and 80.6% (95% CI 52.9, 93.4) for cases with ≥3 LRTD symptoms. For RSV-B associated LRTD across two RSV seasons, descriptive VE was 50.0% (95% CI 18.5, 70.0) for cases with ≥2 LRTD symptoms and 86.4% (95% CI 54.6, 97.4) for cases with ≥3 LRTD symptoms.

14.3 Immunogenicity in Individuals 18 Through 59 Years of Age Considered to be at Increased Risk of LRTD caused by RSV

Study 4 was a Phase 3, multicenter, randomized, double‑blind, placebo‑controlled study to assess the safety and immunogenicity of ABRYSVO in individuals 18 through 59 years of age considered to be at increased risk of LRTD caused by RSV due to chronic medical conditions. Study 4 enrolled individuals who had chronic pulmonary (including asthma), cardiovascular (excluding isolated hypertension), renal, hepatic, neurologic, hematologic or metabolic disorders (including diabetes mellitus and hyper/hypothyroidism) [see Adverse Reactions (6.1)]. Effectiveness was assessed by comparison of the RSV neutralizing geometric mean titers (GMTs) and seroresponse rates of the evaluable immunogenicity population in Study 4 who received ABRYSVO (n=437) to those of a subgroup of individuals from select sites in the United States and Japan in Study 3 (n=410) (Tables 16 and 17). Participants in the Study 3 subgroup were 60 years of age or older; 44% had chronic medical conditions.

Non-inferiority was demonstrated for the ratio of neutralizing GMTs for RSV A and RSV B (Study 4/Study 3 subgroup; lower bounds of the 2‑sided 95% CIs >0.667) (Table 16), and the percentage difference in neutralizing titer seroresponse rates for RSV A and RSV B (Study 4 minus Study 3; lower bounds of the 2‑sided 95% CIs >-10%) (Table 17).

Table 16 Comparison of Model Adjusted RSV Neutralizing GMTs at 1 Month After Vaccination with ABRYSVO, 18 Through 59 Years at Increased Risk of LRTD caused by RSV (Study 4) [NCT05842967] versus 60 Years and Older (Study 3) [NCT05035212]
RSV subgroups | Study 4; 18-59 years of age at high risk; N=435-437; Adjusted GMT [Analysis of covariance adjusted with baseline titer and sex.]; (95% CI) | Study 3; ≥60 years; N=408; Adjusted GMT; (95% CI) | Adjusted GMR, [Non-inferiority was met if the lower bound of the 2-sided CI of adjusted GMR (Study 4/Study3) >0.667 (1.5-fold NI criterion) for both RSV A and RSV B.]; (95% CI)
A | 41097 (37986, 44463) | 26225 (24143, 28486) | 1.57 (1.396, 1.759)
B | 37416 (34278, 40842) | 24680 (22504, 27065) | 1.52 (1.333, 1.725)
CI – confidence interval; GMR – geometric mean ratio; GMT – geometric mean titer

Table 17 Comparison of RSV Neutralizing Titer Seroresponse [Seroresponse is defined as achieving a ≥4-fold rise from baseline if the baseline measurement is above the lower limit of quantitation (LLOQ). If the baseline measurement is below the LLOQ, a post-vaccination assay result ≥4 × LLOQ is considered a seroresponse.] Rates 1 Month After Vaccination with ABRYSVO, 18 Through 59 Years at Increased Risk of LRTD caused by RSV (Study 4) [NCT05842967] versus 60 Years and Older (Study 3) [NCT05035212]
RSV subgroups | Study 4; 18-59 years of age at high risk; N=435-437; % (95% CI) | Study 3; ≥60 years; N=408; % (95% CI) | Percentage Difference [Non-inferiority was met if the lower bound of the 2-sided CI for the percentage difference (Study 4 minus Study 3) >-10% (10% NI criterion) for both RSV A and RSV B.] (95% CI)
A | 93 (90.3, 95.3) | 88 (84.4, 91.0) | 5.1 (1.2, 9.2)
B | 93 (90.6, 95.5) | 85 (81.2, 88.4) | 8.3 (4.2, 12.6)
CI - confidence interval

14.4 Concomitant Administration of ABRYSVO with a Seasonal Inactivated Influenza Vaccine

In Study 5 (NCT05301322) [see Adverse Reactions (6.1)], antibody responses to antigens contained in ABRYSVO and FLUAD QUADRIVALENT were assessed 1 month after vaccination in individuals 65 years of age and older.

Immunologic non-inferiority was demonstrated for concomitant administration of ABRYSVO and FLUAD QUADRIVALENT as compared to sequential administration. The lower limits of the 2-sided 95% CIs for the Geometric Mean Titer Ratio (GMR) (concomitant administration group versus sequential administration group) for RSV A and RSV B neutralizing titers (NT) and hemagglutination inhibition (HAI) titers against influenza strains A/Victoria, A/Darwin, B/Austria, and B/Phuket were above 0.667 (the predefined 1.5-fold non-inferiority criterion).

14.5 Concomitant Administration of ABRYSVO with Tetanus Toxoid, Reduced Diphtheria Toxoid and Acellular Pertussis Vaccine, Adsorbed

Study 6 was a Phase 2, placebo-controlled, randomized, observer-blind study to evaluate the safety, tolerability, and immunogenicity of ABRYSVO (at dose levels 120 µg and 240 µg, with or without Al(OH)3) when administered concomitantly with Tdap in non-pregnant women 18 through 49 years of age.

Antibody responses to antigens contained in ABRYSVO and Tdap were assessed 1 month after vaccination in a population of non-pregnant adult individuals. Lower geometric mean antibody concentrations (GMCs) to the acellular pertussis antigens (pertussis toxin [PT], filamentous hemagglutinin (FHA), and pertactin [PRN]) were observed when ABRYSVO was administered concomitantly with a tetanus, diphtheria and acellular pertussis vaccine (Tdap) compared to pertussis GMCs when Tdap was administered alone. The lower limit (LL) of the 2-sided 95% confidence interval of the GMC ratio (GMC ABRYSVO+Tdap /GMC Tdap) was 0.64 for PT, 0.50 for FHA, and 0.48 for PRN, which did not meet the pre-specified non-inferiority criterion (lower limit of the 95% confidence interval for the GMC ratio is >0.67). The clinical relevance of this finding is unknown. The non-inferiority criteria for tetanus, diphtheria and RSV vaccine antigens were met [see Drug Interactions (7)].

16 HOW SUPPLIED/STORAGE AND HANDLING

16.1 How Supplied

ABRYSVO Act-O-Vial presentation is supplied in cartons of 1 and 10 Act-O-Vials, without syringes or needles. Each Act-O-Vial contains both the Lyophilized Antigen and Sterile Water Diluent (NDC 0069-2465-19).

Carton: 1 Act-O-Vial | NDC 0069-2465-01
Carton: 10 Act-O-Vials | NDC 0069-2465-10

ABRYSVO vial and prefilled syringe presentation is supplied in cartons of 1, 5, and 10 kits, without needles. Each kit includes a vial of Lyophilized Antigen Component (NDC 0069-0207-01), a prefilled syringe containing Sterile Water Diluent Component (NDC 0069-0250-01), and a vial adapter.

Carton: 1 kit | NDC 0069-0344-01
Carton: 5 kits | NDC 0069-0344-05
Carton: 10 kits | NDC 0069-0344-10

ABRYSVO vial and vial presentation is supplied in cartons of 5 and 10 doses packaged without syringes or needles. Each carton includes vials of Lyophilized Antigen Component (NDC 0069-0207-01) and vials of Sterile Water Diluent Component (NDC 0069-0651-01).

Carton: 5 doses | NDC 0069-1265-10
Carton: 10 doses | NDC 0069-1265-20

The Act-O-Vial stoppers, vial stoppers and the tip cap and rubber plunger of the prefilled syringe are not made with natural rubber latex.

16.2 Storage and Handling

Storage Before Reconstitution

Store refrigerated at 2°C to 8°C (36°F to 46°F) in the original carton. Do not freeze. Discard if the carton has been frozen.

Storage After Reconstitution

After reconstitution, administer ABRYSVO immediately or store at room temperature [15ºC to 30ºC (59ºF to 86ºF)] and use within 4 hours. Do not freeze reconstituted vaccine.

17 PATIENT COUNSELING INFORMATION

Prior to administration of this vaccine:

- Inform vaccine recipient of the potential benefits and risks of vaccination with ABRYSVO.
- Advise vaccine recipient to report any adverse events to their healthcare provider or to the Vaccine Adverse Event Reporting System at 1-800-822-7967 and www.vaers.hhs.gov.

This product's labeling may have been updated. For the most recent prescribing information, please visit www.pfizer.com.

Manufactured by
Pfizer Inc.
New York, NY 10001
US License No. 2001

LAB-1498-10.0

PRINCIPAL DISPLAY PANEL - 10 Vial/Syringe Kit Carton

NDC 0069-0344-10
Rx only

NOTICE: Lyophilized Antigen Component and Sterile
Water Diluent Component must be combined before use.

Respiratory Syncytial
Virus Vaccine
ABRYSVO®

For Individuals 60 Years and Older

For Individuals 18 through 59 Years at Increased Risk
for Lower Respiratory Tract Disease caused by RSV

For Pregnant Individuals at 32 through 36 Weeks Gestation

Kit Contents (provides 10 doses of ABRYSVO):
10 vials containing Lyophilized Antigen Component
10 syringes containing Sterile Water Diluent Component
10 vial adapters
After reconstitution, a single dose is approximately 0.5 mL.

Pfizer

PRINCIPAL DISPLAY PANEL - 5 Vial/Syringe Kit Carton

NDC 0069-0344-05
Rx only

NOTICE: Lyophilized Antigen Component and
Sterile Water Diluent Component must be
combined before use.

Respiratory Syncytial
Virus Vaccine
ABRYSVO®

For Individuals 60 Years and Older

For Individuals 18 through 59 Years at Increased Risk
for Lower Respiratory Tract Disease caused by RSV

For Pregnant Individuals at 32 through 36 Weeks Gestation

Kit Contents (provides 5 doses of ABRYSVO):
5 vials containing Lyophilized Antigen Component
5 syringes containing Sterile Water Diluent Component
5 vial adapters
After reconstitution, a single dose is approximately 0.5 mL.

Pfizer

PRINCIPAL DISPLAY PANEL - 1 Vial/Syringe Kit Carton

NDC 0069-0344-01
Rx only

NOTICE: Lyophilized Antigen Component and
Sterile Water Diluent Component must be
combined before use.

Respiratory Syncytial
Virus Vaccine
ABRYSVO®

For Individuals 60 Years and Older

For Individuals 18 through 59 Years at Increased Risk
for Lower Respiratory Tract Disease caused by RSV

For Pregnant Individuals at 32 through 36 Weeks Gestation

Kit Contents (provides a single dose of ABRYSVO):
1 vial containing Lyophilized Antigen Component
1 syringe containing Sterile Water Diluent Component
1 vial adapter
After reconstitution, a single dose is approximately 0.5 mL.

Pfizer

PRINCIPAL DISPLAY PANEL - 0.5 mL Vial Label

NDC 0069-0207-01
Rx only
Lyophilized Antigen Component
NOT TO BE USED ALONE
Reconstitute with Sterile Water Diluent
Component to form Respiratory
Syncytial Virus Vaccine (ABRYSVO®)

Pfizer Inc.
Single dose of approximately
0.5 mL after reconstitution
U.S. Lic.
No. 2001

PRINCIPAL DISPLAY PANEL - 1 Syringe Label

NDC 0069-0250-01

Sterile Water Diluent
Component
NOT TO BE USED ALONE

Add to 1 vial of Lyophilized
Antigen Component to
form Respiratory Syncytial
Virus Vaccine (ABRYSVO®)
U.S. Lic. No. 2001
Pfizer Inc.
Rx only

Lot:
Exp:
OVERPRINT
AREA

PRINCIPAL DISPLAY PANEL – 1 Act-O-Vial Carton

Rx only
NDC 0069-2465-01

NOTICE: Lyophilized Antigen
Component and Sterile Water
Diluent Component must be
combined before use.

Respiratory Syncytial
Virus Vaccine
ABRYSVO®

For Individuals 60 Years
and Older

For Individuals 18 through
59 Years at Increased Risk
for Lower Respiratory Tract
Disease caused by RSV

For Pregnant Individuals
at 32 through 36 Weeks
Gestation

Contents (provides 1 dose of
ABRYSVO): 1 Act-O-Vial
containing Lyophilized Antigen
Component and Sterile Water
Diluent Component

After reconstitution, a single
dose is 0.5 mL.

Pfizer

PRINCIPAL DISPLAY PANEL – 10 Act-O-Vials Carton

Rx only
NDC 0069-2465-10

NOTICE: Lyophilized Antigen Component and Sterile Water
Diluent Component must be combined before use.

Respiratory Syncytial Virus Vaccine
ABRYSVO®

For Individuals 60 Years and Older

For Individuals 18 through 59 Years at Increased Risk
for Lower Respiratory Tract Disease caused by RSV

For Pregnant Individuals at 32 through 36 Weeks Gestation

Contents (provides 10 doses of ABRYSVO): 10 Act-O-Vials each containing
Lyophilized Antigen Component and Sterile Water Diluent Component
After reconstitution, a single dose is 0.5 mL.

Pfizer

PRINCIPAL DISPLAY PANEL – Act-O-Vial Label

NDC 0069-2465-19
Rx only

Act-O-Vial®
Respiratory Syncytial Virus Vaccine
ABRYSVO®

Single dose of 0.5 mL after
reconstitution
Pfizer Inc.
U.S. Lic. No. 2001